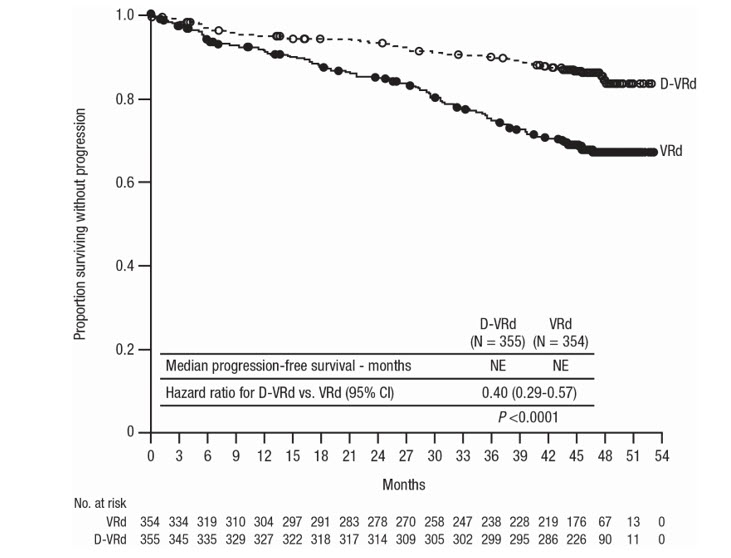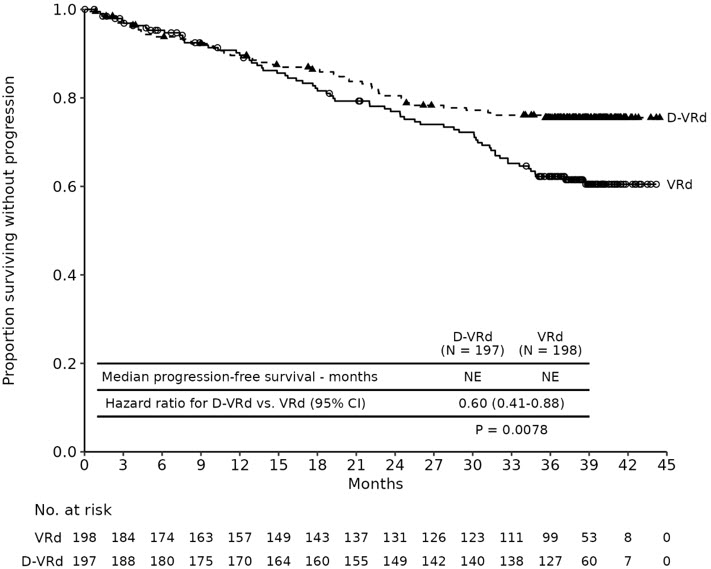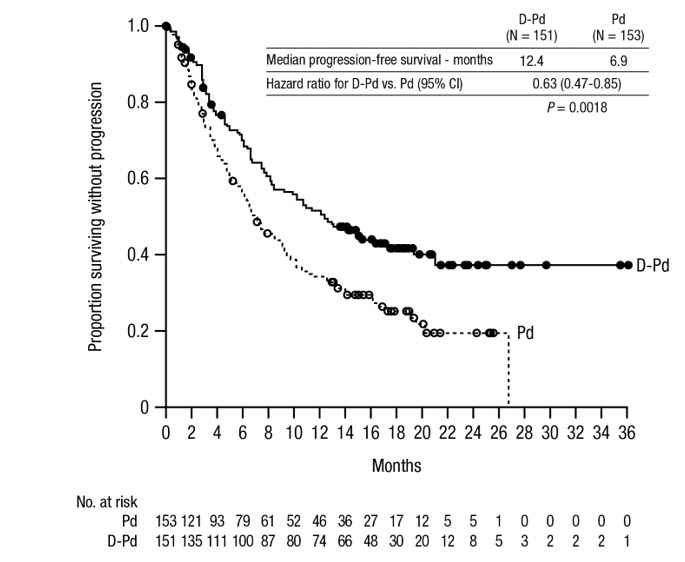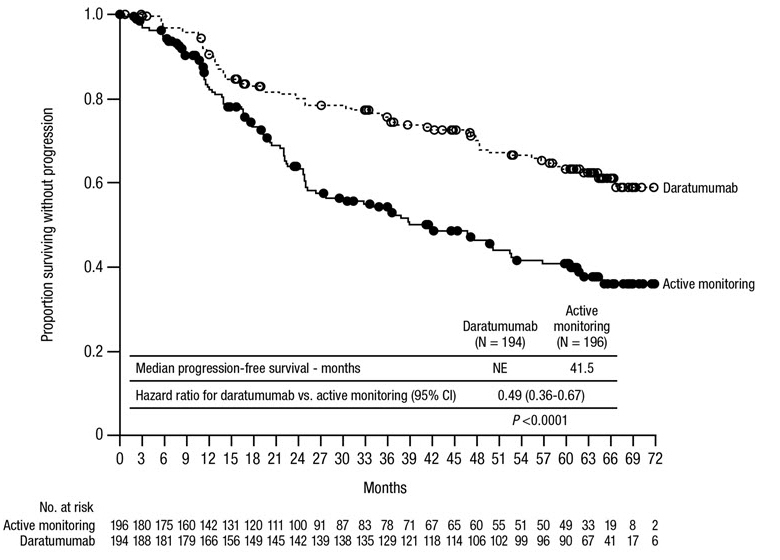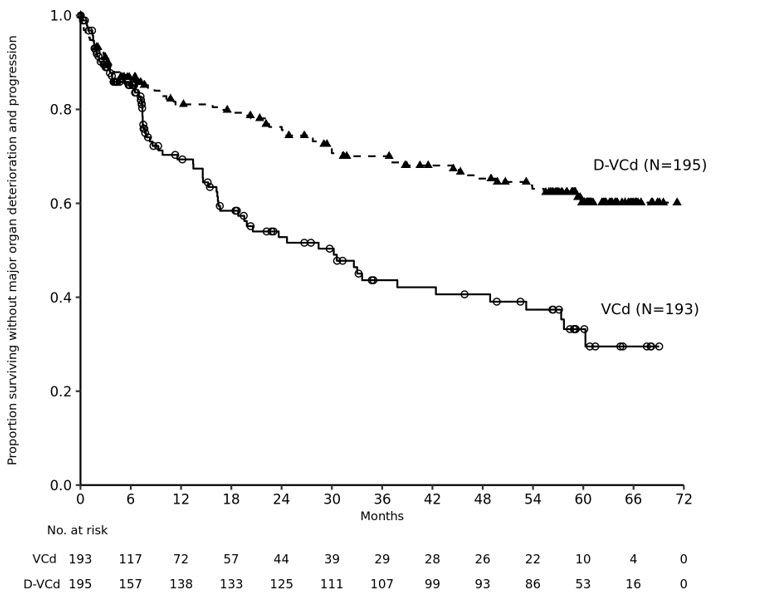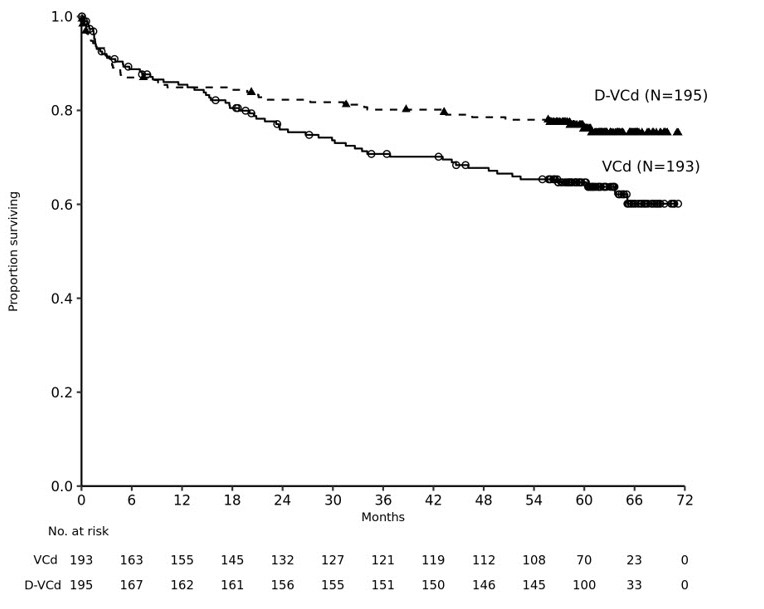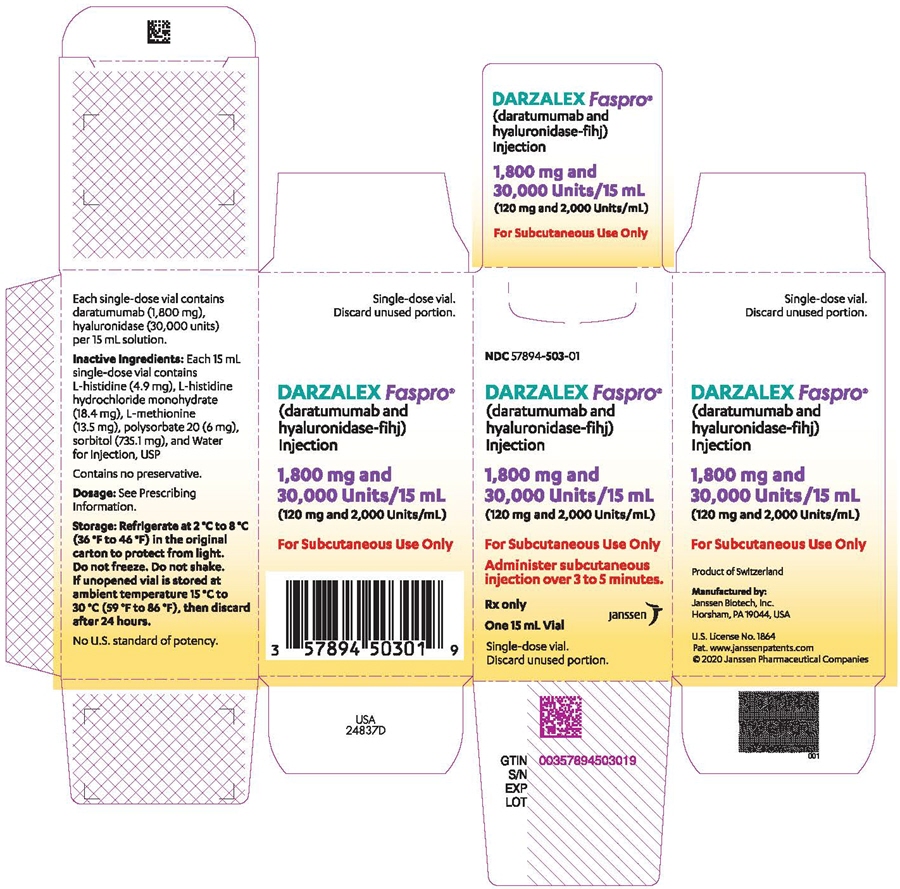 DRUG LABEL: Darzalex Faspro
NDC: 57894-503 | Form: INJECTION
Manufacturer: Janssen Biotech, Inc.
Category: prescription | Type: HUMAN PRESCRIPTION DRUG LABEL
Date: 20260211

ACTIVE INGREDIENTS: DARATUMUMAB 1800 mg/15 mL; HYALURONIDASE (HUMAN RECOMBINANT) 30000 U/15 mL
INACTIVE INGREDIENTS: METHIONINE; HISTIDINE HYDROCHLORIDE MONOHYDRATE; POLYSORBATE 20; SORBITOL; WATER; HISTIDINE

HIGHLIGHTS OF PRESCRIBING INFORMATION

These highlights do not include all the information needed to use DARZALEX FASPRO safely and effectively. See full prescribing information for DARZALEX FASPRO.
DARZALEX FASPRO® (daratumumab and hyaluronidase-fihj) injection, for subcutaneous use
Initial U.S. Approval: 2020

RECENT MAJOR CHANGES

Indications and Usage (1) | 1/2026
Dosage and Administration (2.2) | 1/2026
Dosage and Administration (2.3, 2.8) | 11/2025
Warnings and Precautions (5.1, 5.3) | 11/2025

1 INDICATIONS AND USAGE

DARZALEX FASPRO is a combination of daratumumab, a CD38-directed cytolytic antibody, and hyaluronidase, an endoglycosidase, indicated for the treatment of adult patients with:

- multiple myeloma in combination with bortezomib, lenalidomide, and dexamethasone for induction and consolidation in newly diagnosed patients who are eligible for autologous stem cell transplant
- multiple myeloma in combination with bortezomib, lenalidomide, and dexamethasone in newly diagnosed patients who are ineligible for autologous stem cell transplant
- multiple myeloma in combination with bortezomib, melphalan and prednisone in newly diagnosed patients who are ineligible for autologous stem cell transplant
- multiple myeloma in combination with lenalidomide and dexamethasone in newly diagnosed patients who are ineligible for autologous stem cell transplant and in patients with relapsed or refractory multiple myeloma who have received at least one prior therapy
- multiple myeloma in combination with bortezomib, thalidomide, and dexamethasone in newly diagnosed patients who are eligible for autologous stem cell transplant
- multiple myeloma in combination with bortezomib and dexamethasone in patients who have received at least one prior therapy
- multiple myeloma in combination with pomalidomide and dexamethasone in patients who have received at least one prior line of therapy including lenalidomide and a proteasome inhibitor
- multiple myeloma in combination with carfilzomib and dexamethasone in patients with relapsed or refractory multiple myeloma who have received one to three prior lines of therapy
- multiple myeloma as monotherapy, in patients who have received at least three prior lines of therapy including a proteasome inhibitor (PI) and an immunomodulatory agent or who are double-refractory to a PI and an immunomodulatory agent
- high-risk smoldering multiple myeloma as monotherapy
- light chain (AL) amyloidosis in combination with bortezomib, cyclophosphamide and dexamethasone in newly diagnosed patients.

Limitations of Use:

- DARZALEX FASPRO is not indicated and is not recommended for the treatment of patients with light chain (AL) amyloidosis who have NYHA Class IIIB or Class IV cardiac disease or Mayo Stage IIIB outside of controlled clinical trials (1.3)

2 DOSAGE AND ADMINISTRATION

For subcutaneous use only.

- Pre-medicate with a corticosteroid, acetaminophen and a histamine-1 receptor antagonist. (2.6)
- The recommended dosage of DARZALEX FASPRO is (1,800 mg daratumumab and 30,000 units hyaluronidase) administered subcutaneously into the abdomen over approximately 3 to 5 minutes according to recommended schedule. (2.2, 2.3, 2.4)
- Administer post-medications as recommended. (2.6)

3 DOSAGE FORMS AND STRENGTHS

- Injection: 1,800 mg daratumumab and 30,000 units hyaluronidase per 15 mL (120 mg and 2,000 units/mL) solution in a single-dose vial (3)

4 CONTRAINDICATIONS

Patients with a history of severe hypersensitivity to daratumumab, hyaluronidase or any of the components of the formulation. (4)

5 WARNINGS AND PRECAUTIONS

- Hypersensitivity and Other Administration Reactions: Permanently discontinue DARZALEX FASPRO for life-threatening reactions. (5.1)
- Cardiac Toxicity in Patients with Light Chain (AL) Amyloidosis: Monitor patients with cardiac involvement more frequently for cardiac adverse reactions and administer supportive care as appropriate. (5.2)
- Infections: DARZALEX FASPRO can cause serious and fatal infections. Monitor patients for signs and symptoms of infection and treat appropriately. (5.3)
- Neutropenia: Monitor complete blood cell counts periodically during treatment. Monitor patients with neutropenia for signs of infection. Consider withholding DARZALEX FASPRO to allow recovery of neutrophils. (5.4)
- Thrombocytopenia: Monitor complete blood cell counts periodically during treatment. Consider withholding DARZALEX FASPRO to allow recovery of platelets. (5.5)
- Embryo-Fetal Toxicity: Can cause fetal harm. Advise pregnant women of the potential risk to a fetus and advise females of reproductive potential to use effective contraception. (5.6, 8.1, 8.3)
- Interference with cross-matching and red blood cell antibody screening: Type and screen patients prior to starting treatment. Inform blood banks that a patient has received DARZALEX FASPRO. (5.7, 7.1)

6 ADVERSE REACTIONS

- The most common adverse reactions (≥20%) in patients with multiple myeloma eligible for autologous stem cell transplant who received DARZALEX FASPRO-VRd are peripheral neuropathy, fatigue, upper respiratory infection, constipation, musculoskeletal pain, insomnia, rash, diarrhea, edema, and pyrexia. (6.1)
- The most common adverse reactions (≥20%) in patients with multiple myeloma who were ineligible for autologous stem cell transplant who received DARZALEX FASPRO-VRd are upper respiratory tract infection, sensory neuropathy, musculoskeletal pain, diarrhea, fatigue, edema, rash, motor dysfunction, COVID-19, constipation, sleep disorder, cough, pneumonia, renal impairment, dizziness, nausea, urinary tract infection, pyrexia, abdominal pain, dyspnea, decreased appetite, and bruising. (6.1)
- The most common adverse reaction (≥20%) in patients with multiple myeloma who received DARZALEX FASPRO monotherapy is upper respiratory tract infection. (6.1)
- The most common adverse reactions (≥20%) in patients with multiple myeloma who received DARZALEX FASPRO-VMP are upper respiratory tract infection, constipation, nausea, fatigue, pyrexia, peripheral sensory neuropathy, diarrhea, cough, insomnia, vomiting, and back pain. (6.1)
- The most common adverse reactions (≥20%) in patients with multiple myeloma who received DARZALEX FASPRO-Rd are fatigue, diarrhea, upper respiratory tract infection, muscle spasms, constipation, pyrexia, pneumonia, and dyspnea. (6.1)
- The most common adverse reactions (≥20%) in patients with multiple myeloma who received DARZALEX FASPRO-Pd are fatigue, pneumonia, upper respiratory tract infection, and diarrhea. (6.1)
- The most common adverse reactions (≥20%) in patients with multiple myeloma who received DARZALEX FASPRO-Kd are upper respiratory tract infection, fatigue, insomnia, hypertension, diarrhea, cough, dyspnea, headache, pyrexia, nausea, and edema peripheral. (6.1)
- The most common adverse reactions (≥20%) in patients with high-risk smoldering multiple myeloma who received DARZALEX FASPRO monotherapy are upper respiratory tract infection, musculoskeletal pain, fatigue, diarrhea, rash, sleep disorder, sensory neuropathy, and injection site reactions. (6.1)
- The most common adverse reactions (≥20%) in patients with light chain (AL) amyloidosis are upper respiratory tract infection, diarrhea, peripheral edema, constipation, fatigue, peripheral sensory neuropathy, nausea, insomnia, dyspnea, and cough. (6.1)
- The most common (≥40%) hematology laboratory abnormalities with DARZALEX FASPRO are decreased leukocytes, decreased lymphocytes, decreased neutrophils, decreased platelets, and decreased hemoglobin. (6.1)

To report SUSPECTED ADVERSE REACTIONS, contact Janssen Biotech, Inc. at 1-800-526-7736 (1-800-JANSSEN) or FDA at 1-800-FDA-1088 or www.fda.gov/medwatch.

FULL PRESCRIBING INFORMATION

1 INDICATIONS AND USAGE

1.1 Multiple Myeloma

DARZALEX FASPRO is indicated for the treatment of adult patients with [see Clinical Studies (14)]:

- multiple myeloma in combination with bortezomib, lenalidomide, and dexamethasone for induction and consolidation in newly diagnosed patients who are eligible for autologous stem cell transplant.
- multiple myeloma in combination with bortezomib, lenalidomide, and dexamethasone in newly diagnosed patients who are ineligible for autologous stem cell transplant.
- multiple myeloma in combination with bortezomib, melphalan and prednisone in newly diagnosed patients who are ineligible for autologous stem cell transplant.
- multiple myeloma in combination with lenalidomide and dexamethasone in newly diagnosed patients who are ineligible for autologous stem cell transplant and in patients with relapsed or refractory multiple myeloma who have received at least one prior therapy.
- multiple myeloma in combination with bortezomib, thalidomide, and dexamethasone in newly diagnosed patients who are eligible for autologous stem cell transplant.
- multiple myeloma in combination with bortezomib and dexamethasone in patients who have received at least one prior therapy.
- multiple myeloma in combination with pomalidomide and dexamethasone in patients who have received at least one prior line of therapy including lenalidomide and a proteasome inhibitor.
- multiple myeloma in combination with carfilzomib and dexamethasone in patients with relapsed or refractory multiple myeloma who have received one to three prior lines of therapy.
- multiple myeloma as monotherapy, in patients who have received at least three prior lines of therapy including a proteasome inhibitor (PI) and an immunomodulatory agent or who are double-refractory to a PI and an immunomodulatory agent.

1.2 High-Risk Smoldering Multiple Myeloma

DARZALEX FASPRO as monotherapy is indicated for the treatment of adult patients with high-risk smoldering multiple myeloma.

1.3 Light Chain Amyloidosis

DARZALEX FASPRO in combination with bortezomib, cyclophosphamide and dexamethasone is indicated for the treatment of adult patients with newly diagnosed light chain (AL) amyloidosis.

Limitations of Use

DARZALEX FASPRO is not indicated and is not recommended for the treatment of patients with light chain (AL) amyloidosis who have NYHA Class IIIB or Class IV cardiac disease or Mayo Stage IIIB outside of controlled clinical trials [see Warnings and Precautions (5.2)].

2 DOSAGE AND ADMINISTRATION

2.1 Important Dosing Information

- DARZALEX FASPRO is for subcutaneous use only.
- Administer medications before and after administration of DARZALEX FASPRO to minimize administration-related reactions [see Dosage and Administration (2.6)].
- Type and screen patients prior to starting DARZALEX FASPRO.

2.2 Recommended Dosage for Multiple Myeloma

The recommended dose of DARZALEX FASPRO is 1,800 mg/30,000 units (1,800 mg daratumumab and 30,000 units hyaluronidase) administered subcutaneously over approximately 3 to 5 minutes. Tables 1, 2, 3, 4, 5, and 6 provide the recommended dosing schedule when DARZALEX FASPRO is administered as monotherapy or as part of a combination therapy.

Monotherapy and In Combination with Lenalidomide and Dexamethasone (DARZALEX FASPRO-Rd), Pomalidomide and Dexamethasone (DARZALEX FASPRO-Pd) or Carfilzomib and Dexamethasone (DARZALEX FASPRO-Kd)

Use the dosing schedule provided in Table 1 when DARZALEX FASPRO is administered:

- in combination with lenalidomide and dexamethasone (4-week cycle) OR
- in combination with pomalidomide and dexamethasone (4-week cycle) OR
- in combination with carfilzomib and dexamethasone (4-week cycle) OR
- as monotherapy.

Table 1: DARZALEX FASPRO dosing schedule in combination with lenalidomide, pomalidomide or carfilzomib and dexamethasone (4-week cycle) and for monotherapy
Weeks | Schedule
Weeks 1 to 8 | weekly (total of 8 doses)
Weeks 9 to 24 [First dose of the every-2-week dosing schedule is given at Week 9] | every two weeks (total of 8 doses)
Week 25 onwards until disease progression [First dose of the every-4-week dosing schedule is given at Week 25] | every four weeks

When DARZALEX FASPRO is administered as part of a combination therapy, see Clinical Studies (14.2) and the prescribing information for dosage recommendations for the other drugs.

In Combination with Bortezomib, Melphalan and Prednisone (DARZALEX FASPRO-VMP)

Use the dosing schedule provided in Table 2 when DARZALEX FASPRO is administered in combination with bortezomib, melphalan and prednisone (6-week cycle).

Table 2: DARZALEX FASPRO dosing schedule in combination with bortezomib, melphalan and prednisone (6-week cycle)
Weeks | Schedule
Weeks 1 to 6 | weekly (total of 6 doses)
Weeks 7 to 54 [First dose of the every-3-week dosing schedule is given at Week 7] | every three weeks (total of 16 doses)
Week 55 onwards until disease progression [First dose of the every-4-week dosing schedule is given at Week 55] | every four weeks

When DARZALEX FASPRO is administered as part of a combination therapy, see Clinical Studies (14.1) and the prescribing information for dosage recommendations for the other drugs.

In Combination with Bortezomib, Thalidomide, and Dexamethasone (DARZALEX FASPRO-VTd)

Use the dosing schedule in Table 3 when DARZALEX FASPRO is administered in combination with bortezomib, thalidomide, and dexamethasone (4-week cycle).

Table 3: DARZALEX FASPRO dosing schedule in combination with bortezomib, thalidomide and dexamethasone (4-week cycle)
Treatment phase | Weeks | Schedule
Induction | Weeks 1 to 8 | weekly (total of 8 doses)
Induction | Weeks 9 to 16 [First dose of the every-2-week dosing schedule is given at Week 9] | every two weeks (total of 4 doses)
Stop for high dose chemotherapy and ASCT
Consolidation | Weeks 1 to 8 [First dose of the every-2-week dosing schedule is given at Week 1 upon re-initiation of treatment following ASCT] | every two weeks (total of 4 doses)

When DARZALEX FASPRO is administered as part of a combination therapy, see the prescribing information for dosage recommendations for the other drugs.

In Combination with Bortezomib, Lenalidomide, and Dexamethasone (DARZALEX FASPRO-VRd) for Patients Eligible for Autologous Stem Cell Transplant (ASCT)

Use the dosing schedule in Table 4 when DARZALEX FASPRO is administered in combination with bortezomib, lenalidomide, and dexamethasone (4-week cycle) for treatment of newly diagnosed multiple myeloma patients eligible for ASCT.

Table 4: DARZALEX FASPRO dosing schedule in combination with bortezomib, lenalidomide and dexamethasone (4-week cycle)
Treatment phase | Weeks | Schedule
Induction | Weeks 1 to 8 | weekly (total of 8 doses)
Induction | Weeks 9 to 16 [First dose of the every-2-week dosing schedule is given at Week 9] | every two weeks (total of 4 doses)
Stop for high dose chemotherapy and ASCT
Consolidation | Weeks 1 to 8 [First dose of the every-2-week dosing schedule is given at Week 1 upon re-initiation of treatment following ASCT] | every two weeks (total of 4 doses)

When DARZALEX FASPRO is administered as part of a combination therapy, see Clinical Studies (14.1) and the prescribing information for dosage recommendations for the other drugs.

In Combination with Bortezomib, Lenalidomide, and Dexamethasone (DARZALEX FASPRO-VRd) for Patients Who Are Ineligible for ASCT

Use the dosing schedule in Table 5 when DARZALEX FASPRO is administered in combination with bortezomib, lenalidomide, and dexamethasone (3-week cycle) for treatment of newly diagnosed multiple myeloma patients who are ineligible for ASCT.

Table 5: DARZALEX FASPRO dosing schedule in combination with bortezomib, lenalidomide and dexamethasone (3-week cycle)
Weeks | Schedule
Weeks 1 to 6 | weekly (total of 6 doses)
Weeks 7 to 24 [First dose of the every-3-week dosing schedule is given at Week 7] | every three weeks (total of 6 doses)
Week 25 onwards until disease progression [First dose of the every-4-week dosing schedule is given at Week 25] | every four weeks

When DARZALEX FASPRO is administered as part of a combination therapy, see Clinical Studies (14.1) and the prescribing information for dosage recommendations for the other drugs.

In Combination with Bortezomib and Dexamethasone (DARZALEX FASPRO-Vd)

Use the dosing schedule in Table 6 when DARZALEX FASPRO is administered in combination with bortezomib and dexamethasone (3-week cycle).

Table 6: DARZALEX FASPRO dosing schedule in combination with bortezomib and dexamethasone (3-week cycle)
Weeks | Schedule
Weeks 1 to 9 | weekly (total of 9 doses)
Weeks 10 to 24 [First dose of the every-3-week dosing schedule is given at Week 10] | every three weeks (total of 5 doses)
Week 25 onwards until disease progression [First dose of the every-4-week dosing schedule is given at Week 25] | every four weeks

When DARZALEX FASPRO is administered as part of a combination therapy, see the prescribing information for dosage recommendations for the other drugs.

2.3 Recommended Dosage for High-Risk Smoldering Multiple Myeloma

The recommended dose of DARZALEX FASPRO is 1,800 mg/30,000 units (1,800 mg daratumumab and 30,000 units hyaluronidase) administered subcutaneously over approximately 3 to 5 minutes.

Use the dosing schedule provided in Table 7 when DARZALEX FASPRO is administered as monotherapy in high-risk smoldering multiple myeloma patients (4-week cycle).

Table 7: DARZALEX FASPRO dosing schedule for monotherapy (4-week cycle)
Weeks | Schedule
Weeks 1 to 8 | weekly (total of 8 doses)
Weeks 9 to 24 [First dose of the every-2-week dosing schedule is given at Week 9] | every two weeks (total of 8 doses)
Week 25 onwards until diagnosis of multiple myeloma or a maximum of 3 years [First dose of the every-4-week dosing schedule is given at Week 25] | every four weeks

2.4 Recommended Dosage for Light Chain Amyloidosis

In Combination with Bortezomib, Cyclophosphamide and Dexamethasone (DARZALEX FASPRO-VCd)

The recommended dose of DARZALEX FASPRO is 1,800 mg/30,000 units (1,800 mg daratumumab and 30,000 units hyaluronidase) administered subcutaneously over approximately 3 to 5 minutes.

Use the dosing schedule provided in Table 8 when DARZALEX FASPRO is administered in combination with bortezomib, cyclophosphamide and dexamethasone (4-week cycle).

Table 8: DARZALEX FASPRO dosing schedule in combination with bortezomib, cyclophosphamide and dexamethasone (4-week cycle)
Weeks | Schedule
Weeks 1 to 8 | weekly (total of 8 doses)
Weeks 9 to 24 [First dose of the every-2-week dosing schedule is given at Week 9] | every two weeks (total of 8 doses)
Week 25 onwards until disease progression or a maximum of 2 years [First dose of the every-4-week dosing schedule is given at Week 25] | every four weeks

When DARZALEX FASPRO is administered as part of a combination therapy, see Clinical Studies (14.4) and the prescribing information for dosage recommendations for the other drugs.

2.5 Missed DARZALEX FASPRO Doses

If a dose of DARZALEX FASPRO is missed, administer the dose as soon as possible and adjust the dosing schedule to maintain the dosing interval.

2.6 Recommended Concomitant Medications

Pre-medication

Administer the following pre-medications 1 to 3 hours before each dose of DARZALEX FASPRO:

- Acetaminophen 650 mg to 1,000 mg orally
- Diphenhydramine 25 mg to 50 mg (or equivalent) orally or intravenously
- Corticosteroid (long- or intermediate-acting)
  Monotherapy
  Administer methylprednisolone 100 mg (or equivalent) orally or intravenously. Consider reducing the dose of methylprednisolone to 60 mg (or equivalent) following the second dose of DARZALEX FASPRO.
  In Combination
  Administer dexamethasone 20 mg (or equivalent) orally or intravenously prior to every DARZALEX FASPRO administration.
  When dexamethasone is the background regimen-specific corticosteroid, the dexamethasone dose that is part of the background regimen will serve as pre-medication on DARZALEX FASPRO administration days [see Clinical Studies (14)].
  Do not administer background regimen-specific corticosteroids (e.g., prednisone) on DARZALEX FASPRO administration days when patients have received dexamethasone (or equivalent) as a pre-medication.

Post-medication

Administer the following post-medications:

Monotherapy
  Administer methylprednisolone 20 mg (or an equivalent dose of an intermediate- or long-acting corticosteroid) orally for 2 days starting the day after the administration of DARZALEX FASPRO.
In Combination
  Consider administering oral methylprednisolone at a dose of less than or equal to 20 mg (or an equivalent dose of an intermediate- or long-acting corticosteroid) on the day after administration of DARZALEX FASPRO.
  If a background regimen-specific corticosteroid (e.g., dexamethasone, prednisone) is administered the day after the administration of DARZALEX FASPRO, additional corticosteroids may not be needed [see Clinical Studies (14)].

If the patient does not experience a major systemic administration-related reaction after the first 3 doses of DARZALEX FASPRO, consider discontinuing the administration of corticosteroids (excluding any background regimen-specific corticosteroid).

For patients with a history of chronic obstructive pulmonary disease, consider prescribing short and long-acting bronchodilators and inhaled corticosteroids. Following the first 4 doses of DARZALEX FASPRO, consider discontinuing these additional post-medications, if the patient does not experience a major systemic administration-related reaction.

Prophylaxis for Herpes Zoster Reactivation

Initiate antiviral prophylaxis to prevent herpes zoster reactivation within 1 week after starting DARZALEX FASPRO and continue for 3 months following the end of treatment [see Adverse Reactions (6.1)].

2.7 Dosage Modifications for Adverse Reactions

No dose reductions of DARZALEX FASPRO are recommended. Consider withholding DARZALEX FASPRO to allow recovery of blood cell counts in the event of myelosuppression [see Warnings and Precautions (5.4, 5.5)].

2.8 Preparation and Administration

DARZALEX FASPRO should be administered by a healthcare provider.

To prevent medication errors, check the vial labels to ensure that the drug being prepared and administered is DARZALEX FASPRO for subcutaneous use. Do not administer DARZALEX FASPRO intravenously.

DARZALEX FASPRO is ready to use.

Preparation

- Remove the DARZALEX FASPRO vial from refrigerated storage [2°C to 8°C (36°F to 46°F)] and equilibrate to ambient temperature [15°C to 30°C (59°F to 86°F)]. Store the unpunctured vial at ambient temperature and ambient light for a maximum of 24 hours. Keep out of direct sunlight. Do not shake.
- Withdraw 15 mL from the vial into a syringe using an 18G to 22G transfer needle with a regular bevel. Insert the needle into the vial at a 90° angle within the ring of the stopper.
- Parenteral drug products should be inspected visually for particulate matter and discoloration prior to administration, whenever solution and container permit. Do not use if opaque particles, discoloration or other foreign particles are present.
- DARZALEX FASPRO is compatible with polypropylene or polyethylene syringe material; polypropylene, polyethylene, or polyvinyl chloride (PVC) subcutaneous infusion sets; and stainless steel transfer and injection needles. Use the product immediately.
- After the solution of DARZALEX FASPRO is withdrawn into the syringe, replace the transfer needle with a syringe closing cap. Label the syringe appropriately to include the route of administration per institutional standards. Label the syringe with the peel-off label.
- To avoid needle clogging, attach the hypodermic injection needle or subcutaneous infusion set to the syringe immediately prior to injection.

Storage

- If the syringe containing DARZALEX FASPRO is not used immediately, store refrigerated at 2°C to 8°C (36°F to 46°F) for up to 24 hours and/or at room temperature at 15°C to 25°C (59°F to 77°F) for up to 12 hours under ambient light.
- Discard if storage time exceeds these limits.
- If stored in the refrigerator, allow the solution to come to room temperature before administration.

Administration

- Inject 15 mL of DARZALEX FASPRO into the subcutaneous tissue of the abdomen approximately 3 inches [7.5 cm] to the right or left of the navel over approximately 3 to 5 minutes. No data are available on performing the injection at other sites of the body.
- Rotate injection sites for successive injections.
- Never inject DARZALEX FASPRO into areas where the skin is red, bruised, tender, hard or areas where there are scars.
- Pause or slow down delivery rate if the patient experiences pain. In the event pain is not alleviated by pausing or slowing down delivery rate, a second injection site may be chosen on the opposite side of the abdomen to deliver the remainder of the dose.
- During treatment with DARZALEX FASPRO, do not administer other medications for subcutaneous use at the same site as DARZALEX FASPRO.

3 DOSAGE FORMS AND STRENGTHS

Injection: 1,800 mg daratumumab and 30,000 units hyaluronidase per 15 mL (120 mg and 2,000 units/mL) colorless to yellow and clear to opalescent solution in a single-dose vial.

4 CONTRAINDICATIONS

DARZALEX FASPRO is contraindicated in patients with a history of severe hypersensitivity to daratumumab, hyaluronidase or any of the components of the formulation [see Warnings and Precautions (5.1) and Adverse Reactions (6.2)].

5 WARNINGS AND PRECAUTIONS

5.1 Hypersensitivity and Other Administration Reactions

Both systemic administration-related reactions, including severe or life-threatening reactions, and local injection-site reactions can occur with DARZALEX FASPRO. Fatal reactions have been reported with daratumumab-containing products, including DARZALEX FASPRO [see Adverse Reactions (6.2)].

Systemic Reactions

In a pooled safety population of 1446 patients with multiple myeloma (N=1253) or light chain (AL) amyloidosis (N=193) who received DARZALEX FASPRO as monotherapy or as part of a combination therapy, 7% of patients experienced a systemic administration-related reaction (Grade 2: 3%, Grade 3: 0.8%, Grade 4: 0.1%). In patients with high-risk smoldering multiple myeloma (N=193), systemic administration-related reactions occurred in 17% of patients in AQUILA (Grade 2: 7%, Grade 3: 1%).

In all patients (N=1639), systemic administration-related reactions occurred in 7% of patients with the first injection, 0.5% with the second injection, and cumulatively 1% with subsequent injections. The median time to onset was 3.2 hours (range: 4 minutes to 3.5 days). Of the 283 systemic administration-related reactions that occurred in 135 patients, 240 (85%) occurred on the day of DARZALEX FASPRO administration. Delayed systemic administration-related reactions have occurred in 1% of the patients.

Severe reactions include hypoxia, dyspnea, hypertension, and tachycardia, and ocular adverse reactions, including choroidal effusion, acute myopia, and acute angle closure glaucoma. Other signs and symptoms of systemic administration-related reactions may include respiratory symptoms, such as bronchospasm, nasal congestion, cough, throat irritation, allergic rhinitis, and wheezing, as well as anaphylactic reaction, pyrexia, chest pain, pruritus, chills, vomiting, nausea, hypotension, and blurred vision.

Pre-medicate patients with histamine-1 receptor antagonist, acetaminophen and corticosteroids [see Dosage and Administration (2.6)]. Monitor patients for systemic administration-related reactions, especially following the first and second injections. For anaphylactic reaction or life-threatening (Grade 4) administration-related reactions, immediately and permanently discontinue DARZALEX FASPRO. Consider administering corticosteroids and other medications after the administration of DARZALEX FASPRO depending on dosing regimen and medical history to minimize the risk of delayed (defined as occurring the day after administration) systemic administration-related reactions [see Dosage and Administration (2.6)].

Ocular adverse reactions, including acute myopia and narrowing of the anterior chamber angle due to ciliochoroidal effusions with potential for increased intraocular pressure or glaucoma, have occurred with daratumumab-containing products. If ocular symptoms occur, interrupt DARZALEX FASPRO and seek immediate ophthalmologic evaluation prior to restarting DARZALEX FASPRO.

Local Reactions

In this pooled safety population of 1446 patients with multiple myeloma (N=1253) or light chain (AL) amyloidosis (N=193), injection-site reactions occurred in 8% of patients, including Grade 2 reactions in 1.1%. The most frequent (>1%) injection-site reactions were injection site erythema and injection site rash. In patients with high-risk smoldering multiple myeloma (N=193), injection-site reactions occurred in 28% of patients, including Grade 2 reactions in 3%. These local reactions occurred a median of 6 minutes (range: 0 minutes to 6.5 days) after starting administration of DARZALEX FASPRO. Monitor for local reactions and consider symptomatic management.

5.2 Cardiac Toxicity in Patients with Light Chain (AL) Amyloidosis

Serious or fatal cardiac adverse reactions occurred in patients with light chain (AL) amyloidosis who received DARZALEX FASPRO in combination with bortezomib, cyclophosphamide and dexamethasone [see Adverse Reactions (6.1)]. Serious cardiac disorders occurred in 16% and fatal cardiac disorders occurred in 10% of patients. Patients with NYHA Class IIIA or Mayo Stage IIIA disease may be at greater risk. Patients with NYHA Class IIIB or IV disease were not studied.

Monitor patients with cardiac involvement of light chain (AL) amyloidosis more frequently for cardiac adverse reactions and administer supportive care as appropriate.

5.3 Infections

DARZALEX FASPRO can cause serious, life-threatening, or fatal infections. In patients who received DARZALEX FASPRO in a pooled safety population including patients with smoldering multiple myeloma and light chain (AL) amyloidosis (N=1639), serious infections, including opportunistic infections, occurred in 24% of patients, Grade 3 or 4 infections occurred in 22%, and fatal infections occurred in 2.5%. The most common type of serious infection reported was pneumonia (8.5%).

Monitor patients for signs and symptoms of infection prior to and during treatment with DARZALEX FASPRO and treat appropriately. Administer prophylactic antimicrobials according to guidelines [see Dosage and Administration (2.6)].

5.4 Neutropenia

Daratumumab may increase neutropenia induced by background therapy [see Adverse Reactions (6.1)].

Monitor complete blood cell counts periodically during treatment according to manufacturer's prescribing information for background therapies. Monitor patients with neutropenia for signs of infection. Consider withholding DARZALEX FASPRO until recovery of neutrophils. In lower body weight patients receiving DARZALEX FASPRO, higher rates of Grade 3–4 neutropenia were observed.

5.5 Thrombocytopenia

Daratumumab may increase thrombocytopenia induced by background therapy [see Adverse Reactions (6.1)].

Monitor complete blood cell counts periodically during treatment according to manufacturer's prescribing information for background therapies. Consider withholding DARZALEX FASPRO until recovery of platelets.

5.6 Embryo-Fetal Toxicity

Based on the mechanism of action, DARZALEX FASPRO can cause fetal harm when administered to a pregnant woman. DARZALEX FASPRO may cause depletion of fetal immune cells and decreased bone density. Advise pregnant women of the potential risk to a fetus. Advise females with reproductive potential to use effective contraception during treatment with DARZALEX FASPRO and for 3 months after the last dose [see Use in Specific Populations (8.1, 8.3)].

The combination of DARZALEX FASPRO with lenalidomide, thalidomide or pomalidomide is contraindicated in pregnant women, because lenalidomide, thalidomide or pomalidomide may cause birth defects and death of the unborn child. Refer to the lenalidomide, thalidomide or pomalidomide prescribing information on use during pregnancy.

5.7 Interference with Serological Testing

Daratumumab binds to CD38 on red blood cells (RBCs) and results in a positive Indirect Antiglobulin Test (Indirect Coombs test). Daratumumab-mediated positive indirect antiglobulin test may persist for up to 6 months after the last daratumumab administration. Daratumumab bound to RBCs masks detection of antibodies to minor antigens in the patient's serum [see References (15)]. The determination of a patient's ABO and Rh blood type are not impacted [see Drug Interactions (7.1)].

Notify blood transfusion centers of this interference with serological testing and inform blood banks that a patient has received DARZALEX FASPRO. Type and screen patients prior to starting DARZALEX FASPRO [see Dosage and Administration (2.1)].

5.8 Interference with Determination of Complete Response

Daratumumab is a human IgG kappa monoclonal antibody that can be detected on both the serum protein electrophoresis (SPE) and immunofixation (IFE) assays used for the clinical monitoring of endogenous M-protein [see Drug Interactions (7.1)]. This interference can impact the determination of complete response and of disease progression in some DARZALEX FASPRO-treated patients with IgG kappa myeloma protein.

6 ADVERSE REACTIONS

The following clinically significant adverse reactions are described elsewhere in the labeling:

- Hypersensitivity and Other Administration Reactions [see Warnings and Precautions (5.1)].
- Cardiac Toxicity in Patients with Light Chain (AL) Amyloidosis [see Warnings and Precautions (5.2)].
- Infections [see Warnings and Precautions (5.3)].
- Neutropenia [see Warnings and Precautions (5.4)].
- Thrombocytopenia [see Warnings and Precautions (5.5)].

6.1 Clinical Trials Experience

Because clinical trials are conducted under widely varying conditions, adverse reaction rates observed in the clinical trials of a drug cannot be directly compared to rates in the clinical trials of another drug and may not reflect the rates observed in practice.

Newly Diagnosed Multiple Myeloma Eligible for Autologous Stem Cell Transplant

In Combination with Bortezomib, Lenalidomide and Dexamethasone

The safety of DARZALEX FASPRO in combination with bortezomib, lenalidomide and dexamethasone (n=351) from the start of induction to the end of consolidation compared to bortezomib, lenalidomide and dexamethasone (VRd) (n=347) was evaluated in PERSEUS [see Clinical Studies (14.1)]. Patients received DARZALEX FASPRO 1,800 mg/30,000 units administered subcutaneously once weekly from weeks 1 to 8 and once every 2 weeks from weeks 9 to 16 during induction in combination with VRd or VRd alone. After week 16, patients underwent stem cell mobilization, high dose chemotherapy, and ASCT. Within 12 weeks of ASCT, and when engraftment was complete, patients received DARZALEX FASPRO once every 2 weeks from weeks 1 to 8 during consolidation in combination with VRd or VRd alone.

The median duration of treatment for induction and consolidation was 9.9 months (0.5 to 18.5 months) for DARZALEX FASPRO-VRd.

Serious adverse reactions occurred in 37% of patients who received DARZALEX FASPRO-VRd. The most frequent serious adverse reaction in >5% of patients who received DARZALEX FASPRO-VRd was pneumonia (6%). Fatal adverse reactions occurred in 1.7% of patients who received DARZALEX FASPRO-VRd.

Permanent treatment discontinuation due to an adverse reaction occurred in 2% of patients who received DARZALEX FASPRO-VRd. An adverse reaction which resulted in permanent discontinuation of DARZALEX FASPRO-VRd in more than 1 patient included sepsis.

The most common adverse reactions (≥20%) were peripheral neuropathy, fatigue, upper respiratory infection, constipation, musculoskeletal pain, insomnia, rash, diarrhea, edema, and pyrexia.

Table 9 summarizes the adverse reactions in patients who received DARZALEX FASPRO in PERSEUS.

Table 9: Adverse Reactions (≥10%) in Patients Who Received DARZALEX FASPRO-VRd through the End of Consolidation in PERSEUS
Adverse Reaction | DARZALEX FASPRO-VRd (N=351) |  | VRd (N=347)
Adverse Reaction | All Grades (%) | Grade 3 or 4 (%) | All Grades (%) | Grade 3 or 4 (%)
Nervous system disorders
Peripheral neuropathy [Peripheral neuropathy includes neuropathy peripheral, peripheral motor neuropathy, peripheral sensorimotor neuropathy, and peripheral sensory neuropathy.] | 52 | 5 | 54 | 4
Paresthesia | 11 | <1 [Only Grade 3 adverse reactions occurred.] | 11 | <1
General disorders and administration site conditions
Fatigue [Includes other related terms.] | 35 | 3 | 37 | 5
Edema | 22 | 1 | 21 | 1
Pyrexia | 21 | 2 | 22 | 3
Infections
Upper respiratory tract infection [Upper respiratory tract infection includes fungal pharyngitis, h1n1 influenza, influenza, influenza like illness, laryngitis, nasopharyngitis, oral candidiasis, oropharyngeal candidiasis, parainfluenzae virus infection, pharyngitis, respiratory moniliasis, respiratory syncytial virus infection, respiratory tract infection, respiratory tract infection viral, rhinitis, rhinovirus infection, sinusitis, tonsillitis, upper respiratory tract infection, viral tonsillitis, and viral upper respiratory tract infection.] | 32 | 1 | 26 | 2
Pneumonia [Pneumonia includes bronchopulmonary aspergillosis, lower respiratory tract infection, pneumocystis jirovecii pneumonia, pneumonia, pneumonia bacterial, pneumonia cytomegaloviral, pneumonia influenzal, pneumonia klebsiella, pneumonia legionella, and pneumonia streptococcal.] | 14 | 9 | 10 | 6 [Fatal adverse reactions included Pneumonia: n=1 (0.3%) in the VRd arm.]
Gastrointestinal disorders
Constipation | 31 | 2 | 30 | 2
Diarrhea | 23 | 3 | 25 | 5
Nausea | 16 | 1 | 12 | 1
Abdominal pain | 11 | 0 | 12 | 0
Musculoskeletal and connective tissue disorders
Musculoskeletal pain | 26 | 1 | 23 | 1
Muscle spasm | 12 | 0 | 9 | <1
Psychiatric disorders
Insomnia | 26 | 2 | 16 | 2
Skin and subcutaneous tissue disorders
Rash | 25 | 3 | 31 | 5
Hepatobiliary disorders
Hepatotoxicity [Hepatotoxicity includes alanine aminotransferase increased, aspartate aminotransferase increased, hepatic cytolysis, hepatic failure, hepatic function abnormal, hepatotoxicity, hyperbilirubinemia, hypertransaminasemia, and liver disorder] | 16 | 6 | 16 | 5
Respiratory, thoracic and mediastinal disorders
Cough | 12 | <1 | 8 | 0
Key: VRd=bortezomib-lenalidomide-dexamethasone

Clinically relevant adverse reactions in <10% of patients who received DARZALEX FASPRO with bortezomib, lenalidomide and dexamethasone include:

- Gastrointestinal disorders: vomiting, hemorrhoids
- Musculoskeletal and connective tissue disorders: arthralgia
- Infections: bronchitis, sepsis, urinary tract infection, herpes zoster, Covid-19, cytomegalovirus infection
- Respiratory, thoracic, and mediastinal disorders: dyspnea, pulmonary edema
- Metabolism and nutrition disorders: hypocalcemia, decreased appetite, hyperglycemia, dehydration
- Vascular disorders: hypotension, hypertension, orthostatic hypotension
- General disorders and administration site conditions: infusion reactions, injection site reaction, chills
- Nervous system disorders: dizziness, headache, syncope
- Cardiac disorders: thrombosis, atrial fibrillation, tachycardia
- Skin and subcutaneous tissue disorders: pruritus

Table 10 summarizes the laboratory abnormalities in patients who received DARZALEX FASPRO in PERSEUS.

Table 10: Select Laboratory Abnormalities (≥30%) That Worsened from Baseline in Patients Who Received DARZALEX FASPRO-VRd through the End of Consolidation in PERSEUS
Laboratory Abnormality | DARZALEX FASPRO-VRd [Denominator is based on number of subjects with a baseline and post-baseline laboratory value for each laboratory test: N=351 for DARZALEX FASPRO-VRd and N=346 for VRd.] |  | VRd
Laboratory Abnormality | All Grades (%) | Grade 3 or4 (%) | All Grades (%) | Grade 3 or 4 (%)
Hematology
Decreased platelets | 89 | 34 | 78 | 25
Decreased lymphocytes | 87 | 69 | 69 | 43
Decreased leukocytes | 78 | 47 | 56 | 22
Decreased neutrophils | 67 | 52 | 47 | 34
Decreased hemoglobin | 39 | 7 | 43 | 6
Chemistry
Increased alanine aminotransferase (ALT) | 52 | 7 | 48 | 5
Decreased sodium | 40 | 5 | 25 | 5
Increased alkaline phosphatase | 39 | 0 | 36 | 1
Decreased potassium | 30 | 6 | 24 | 3
Key: VRd=bortezomib-lenalidomide-dexamethasone

Newly Diagnosed Multiple Myeloma Ineligible for Autologous Stem Cell Transplant

In Combination with Bortezomib, Lenalidomide and Dexamethasone

The safety of DARZALEX FASPRO in combination with bortezomib, lenalidomide and dexamethasone compared to bortezomib, lenalidomide and dexamethasone (VRd) was evaluated in CEPHEUS in patients with newly diagnosed multiple myeloma who were ineligible for ASCT or refused ASCT as initial therapy [see Clinical Studies (14.1)]. Patients received DARZALEX FASPRO 1,800 mg/30,000 units administered subcutaneously once weekly from weeks 1 to 6, once every 3 weeks from weeks 7 to 24 and once every 4 weeks starting with week 25 until disease progression or unacceptable toxicity in combination with VRd (n=197) or VRd alone (n=195).

The median duration of treatment was 56.3 months (0.1 to 64.6 months) for DARZALEX FASPRO-VRd and 34.3 months (0.5 to 63.8 months) for VRd.

Serious adverse reactions occurred in 72% of patients who received DARZALEX FASPRO-VRd. The most frequent serious adverse reactions in >5% of patients who received DARZALEX FASPRO-VRd were pneumonia (19%), COVID-19 (12%), thromboembolism (7%), and diarrhea (6%). Fatal adverse reactions occurred in 16.8% of patients who received DARZALEX FASPRO-VRd. Fatal adverse reactions that occurred in more than 1 patient included pneumonia (4%), COVID-19 (4%), and myocardial infarction (2%).

Permanent treatment discontinuation due to an adverse reaction occurred in 8% of patients who received DARZALEX FASPRO-VRd. An adverse reaction which resulted in permanent discontinuation of DARZALEX FASPRO-VRd in more than 1 patient included pneumonia.

The most common adverse reactions (≥20%) were upper respiratory tract infection, sensory neuropathy, musculoskeletal pain, diarrhea, fatigue, edema, rash, motor dysfunction, COVID-19, constipation, sleep disorder, cough, pneumonia, renal impairment, dizziness, nausea, urinary tract infection, pyrexia, abdominal pain, dyspnea, decreased appetite, and bruising.

Table 11 summarized the adverse reactions in patients who received DARZALEX FASPRO in CEPHEUS.

Table 11: Adverse Reactions Reported in ≥20% of Patients Who Received DARZALEX FASPRO-VRd in CEPHEUS
Adverse Reaction | DARZALEX FASPRO-VRd (N=197) |  | VRd (N=195)
Adverse Reaction | All Grades (%) | Grade 3 or 4 (%) | All Grades (%) | Grade 3 or 4 (%)
Infections
Upper respiratory tract infection [Upper respiratory tract infection includes acute sinusitis, influenza, influenza like illness, laryngitis, nasal congestion, nasopharyngitis, parainfluenzae virus infection, pharyngitis, pharyngitis streptococcal, respiratory syncytial virus infection, respiratory tract infection, respiratory tract infection bacterial, respiratory tract infection viral, rhinitis, rhinovirus infection, sinus congestion, sinus disorder, sinusitis, tonsillitis, tracheitis, upper respiratory tract infection, upper respiratory tract inflammation, and viral upper respiratory tract infection.] | 75 | 4 [Only Grade 3 adverse reactions occurred.] | 63 | 3
COVID-19 [Includes other related terms.] | 39 [Fatal adverse reactions occurred for Abdominal pain: n=1 (1%) in the DARZALEX FASPRO-VRd arm; COVID-19: n=7 (4%) in the DARZALEX FASPRO-VRd arm and n=5 (3%) in the VRd arm; Pneumonia: n=8 (4%) in the DARZALEX FASPRO-VRd arm and n=5 (3%) in the VRd arm; Dyspnea: n=1 (1%) in the DARZALEX FASPRO-VRd arm.] | 9 | 25 | 3
Pneumonia [Pneumonia includes bronchopulmonary aspergillosis, covid-19 pneumonia, lower respiratory tract infection, pneumocystis jirovecii pneumonia, pneumonia, pneumonia aspiration, pneumonia bacterial, pneumonia cryptococcal, pneumonia influenzal, pneumonia klebsiella, pneumonia legionella, pneumonia pneumococcal, pneumonia respiratory syncytial viral, pneumonia viral, and tuberculosis.] | 31 | 16 | 26 | 15
Urinary tract infection | 24 | 4 | 17 | 3
Nervous system disorders
Sensory neuropathy [Sensory neuropathy includes anosmia, burning sensation, dysesthesia, hyperesthesia, hyperesthesia teeth, hypoesthesia, hypoesthesia oral, neuralgia, neuropathy peripheral, oral dysesthesia, palmar-plantar erythrodysesthesia syndrome, paresthesia, paresthesia oral, peripheral sensorimotor neuropathy, peripheral sensory neuropathy, polyneuropathy, and skin burning sensation.] | 72 | 12 | 72 | 10
Motor dysfunction [Motor dysfunction includes balance disorder, essential tremor, extrapyramidal disorder, facial paralysis, gait disturbance, hypotonia, mobility decreased, motor dysfunction, muscle contractions involuntary, muscle contracture, muscle spasms, muscular weakness, myopathy, paraparesis, peripheral motor neuropathy, peroneal nerve palsy, pharyngeal paresthesia, and tremor.] | 44 | 11 | 37 | 7
Dizziness | 26 | 2 | 26 | 1
Musculoskeletal and connective tissue disorders
Musculoskeletal pain | 62 | 9 | 61 | 7
Gastrointestinal disorders
Diarrhea | 57 | 12 | 59 | 9
Constipation | 38 | 2 | 42 | 3
Nausea | 25 | 0 | 25 | 2
Abdominal pain | 23 | 1 | 17 | 2
General disorders and administration site conditions
Fatigue | 56 | 14 | 53 | 11
Edema | 54 | 4 | 46 | 2
Pyrexia | 24 | 1 | 16 | 1
Skin and subcutaneous tissue disorders
Rash | 50 | 8 | 47 | 7
Psychiatric disorders
Sleep disorder | 33 | 3 | 33 | 2
Respiratory, thoracic and mediastinal disorders
Cough | 32 | 1 | 21 | 1
Dyspnea | 21 | 2 | 17 | 1
Renal and urinary disorders
Renal impairment [Renal impairment includes acute kidney injury, blood creatinine increased, chronic kidney disease, creatinine renal clearance decreased, glomerular filtration rate decreased, prerenal failure, renal failure, renal impairment, and renal injury.] | 26 | 7 | 25 | 6
Metabolism and nutrition disorders
Decreased appetite | 21 | 1 | 20 | 3
Injury, poisoning and procedural complications
Bruising | 20 | 0 | 12 | 0
Key: VRd=bortezomib-lenalidomide dexamethasone

Clinically relevant adverse reactions in <20% of patients who received DARZALEX FASPRO with bortezomib, lenalidomide and dexamethasone include:

- Infections: bronchitis, sepsis, herpes zoster, hepatitis B reactivation
- Gastrointestinal disorders: vomiting, pancreatitis
- Metabolism and nutrition disorders: hyperglycemia
- Vascular disorders: hypertension, hypotension, thromboembolism, hemorrhage
- Nervous system disorders: headache, syncope
- General disorders and administration site conditions: chills, infusion reactions, injection site reactions
- Cardiac disorders: atrial fibrillation
- Skin and subcutaneous tissue disorders: pruritus

Table 12 summarizes the laboratory abnormalities in patients who received DARZALEX FASPRO in CEPHEUS.

Table 12: Select Laboratory Abnormalities (≥30%) That Worsened from Baseline in Patients Who Received DARZALEX FASPRO-VRd in CEPHEUS
Laboratory Abnormality | DARZALEX FASPRO-VRd [Denominator is based on number of subjects with a baseline and post-baseline laboratory value for each laboratory test: N=197 for DARZALEX FASPRO-VRd and N=194 for VRd.] |  | VRd
Laboratory Abnormality | All Grades (%) | Grade 3 or 4 (%) | All Grades (%) | Grade 3 or 4 (%)
Hematology
Decreased leukocytes | 93 | 39 | 77 | 15
Decreased neutrophils | 89 | 49 | 75 | 35
Decreased lymphocytes | 87 | 55 | 72 | 38
Decreased platelets | 81 | 31 | 73 | 23
Decreased hemoglobin | 53 | 14 | 52 | 16
Chemistry
Increased alanine aminotransferase (ALT) | 66 | 7 | 61 | 3
Increased creatinine | 54 | 5 | 56 | 3
Decreased potassium | 53 | 19 | 36 | 12
Decreased sodium | 48 | 16 | 40 | 13
Increased aspartate aminotransferase (AST) | 43 | 3 | 46 | 3
Increased alkaline phosphatase | 43 | 2 | 31 | 1
Decreased corrected calcium | 32 | 5 | 26 | 5
Key: VRd=bortezomib-lenalidomide-dexamethasone

Newly Diagnosed Multiple Myeloma Ineligible for Autologous Stem Cell Transplant

In Combination with Bortezomib, Melphalan and Prednisone

The safety of DARZALEX FASPRO with bortezomib, melphalan and prednisone was evaluated in a single-arm cohort of PLEIADES [see Clinical Studies (14.1)]. Patients received DARZALEX FASPRO 1,800 mg/30,000 units administered subcutaneously once weekly from weeks 1 to 6, once every 3 weeks from weeks 7 to 54 and once every 4 weeks starting with week 55 until disease progression or unacceptable toxicity (N=67) in combination with bortezomib, melphalan and prednisone. Among these patients, 93% were exposed for 6 months or longer and 19% were exposed for greater than one year.

Serious adverse reactions occurred in 39% of patients who received DARZALEX FASPRO. Serious adverse reactions in >5% of patients included pneumonia and pyrexia. Fatal adverse reactions occurred in 3% of patients.

Permanent discontinuation of DARZALEX FASPRO due to an adverse reaction occurred in 4.5% of patients. The adverse reaction resulting in permanent discontinuation of DARZALEX FASPRO in more than 1 patient was neutropenic sepsis.

Dosage interruptions (defined as dose delays or skipped doses) due to an adverse reaction occurred in 51% of patients who received DARZALEX FASPRO. Adverse reactions requiring dosage interruptions in >5% of patients included thrombocytopenia, neutropenia, anemia, and pneumonia.

The most common adverse reactions (≥20%) were upper respiratory tract infection, constipation, nausea, fatigue, pyrexia, peripheral sensory neuropathy, diarrhea, cough, insomnia, vomiting, and back pain.

Table 13 summarizes the adverse reactions in patients who received DARZALEX FASPRO in PLEIADES.

Table 13: Adverse Reactions (≥10%) in Patients Who Received DARZALEX FASPRO with Bortezomib, Melphalan and Prednisone (DARZALEX FASPRO-VMP) in PLEIADES
Adverse Reaction | DARZALEX FASPRO with Bortezomib, Melphalan and Prednisone (N=67)
Adverse Reaction | All Grades (%) | Grades ≥3 (%)
Infections
Upper respiratory tract infection [Upper respiratory tract infection includes nasopharyngitis, respiratory syncytial virus infection, respiratory tract infection, rhinitis, tonsillitis, upper respiratory tract infection, and viral pharyngitis.] | 39 | 0
Bronchitis | 16 | 0
Pneumonia [Pneumonia includes lower respiratory tract infection, lung infection, pneumocystis jirovecii pneumonia, pneumonia, and pneumonia bacterial.] | 15 | 7 [Only Grade 3 adverse reactions occurred.]
Gastrointestinal disorders
Constipation | 37 | 0
Nausea | 36 | 0
Diarrhea | 33 | 3
Vomiting | 21 | 0
Abdominal pain [Abdominal pain includes abdominal pain, and abdominal pain upper.] | 13 | 0
General disorders and administration site conditions
Fatigue [Fatigue includes asthenia, and fatigue.] | 36 | 3
Pyrexia | 34 | 0
Edema peripheral [Edema peripheral includes edema, edema peripheral, and peripheral swelling.] | 13 | 1
Nervous system disorders
Peripheral sensory neuropathy | 34 | 1
Dizziness | 10 | 0
Respiratory, thoracic and mediastinal disorders
Cough [Cough includes cough, and productive cough.] | 24 | 0
Psychiatric disorders
Insomnia | 22 | 3
Musculoskeletal and connective tissue disorders
Back pain | 21 | 3
Musculoskeletal chest pain | 12 | 0
Metabolism and nutrition disorders
Decreased appetite | 15 | 1
Skin and subcutaneous tissue disorders
Rash | 13 | 0
Pruritus | 12 | 0
Vascular disorders
Hypertension | 13 | 6
Hypotension | 10 | 3

Clinically relevant adverse reactions in <10% of patients who received DARZALEX FASPRO with bortezomib, melphalan and prednisone included:

- General disorders and administration site conditions: infusion reaction, injection site reaction, chills
- Infections: herpes zoster, urinary tract infection, influenza, sepsis
- Musculoskeletal and connective tissue disorders: arthralgia, muscle spasms
- Nervous system disorders: headache, paresthesia
- Metabolism and nutrition disorders: hypocalcemia, hyperglycemia
- Respiratory, thoracic and mediastinal disorders: dyspnea, pulmonary edema
- Cardiac disorders: atrial fibrillation

Table 14 summarizes the laboratory abnormalities in patients who received DARZALEX FASPRO in PLEIADES.

Table 14: Select Hematology Laboratory Abnormalities Worsening from Baseline in Patients Who Received DARZALEX FASPRO with Bortezomib, Melphalan and Prednisone (DARZALEX FASPRO-VMP) in PLEIADES
Laboratory Abnormality | DARZALEX FASPRO with Bortezomib, Melphalan and Prednisone [Denominator is based on the safety population treated with DARZALEX FASPRO-VMP (N=67).]
Laboratory Abnormality | All Grades (%) | Grades 3–4 (%)
Decreased leukocytes | 96 | 52
Decreased lymphocytes | 93 | 84
Decreased platelets | 93 | 42
Decreased neutrophils | 88 | 49
Decreased hemoglobin | 48 | 19

Relapsed/Refractory Multiple Myeloma

In Combination with Lenalidomide and Dexamethasone

The safety of DARZALEX FASPRO with lenalidomide and dexamethasone was evaluated in a single-arm cohort of PLEIADES [see Clinical Studies (14.2)]. Patients received DARZALEX FASPRO 1,800 mg/30,000 units administered subcutaneously once weekly from weeks 1 to 8, once every 2 weeks from weeks 9 to 24 and once every 4 weeks starting with week 25 until disease progression or unacceptable toxicity (N=65) in combination with lenalidomide and dexamethasone. Among these patients, 92% were exposed for 6 months or longer and 20% were exposed for greater than one year.

Serious adverse reactions occurred in 48% of patients who received DARZALEX FASPRO. Serious adverse reactions in >5% of patients included pneumonia, influenza and diarrhea. Fatal adverse reactions occurred in 3.1% of patients.

Permanent discontinuation of DARZALEX FASPRO due to an adverse reaction occurred in 11% of patients who received DARZALEX FASPRO. Adverse reactions resulting in permanent discontinuation of DARZALEX FASPRO in more than 1 patient were pneumonia and anemia.

Dosage interruptions due to an adverse reaction occurred in 63% of patients who received DARZALEX FASPRO. Adverse reactions requiring dosage interruptions in >5% of patients included neutropenia, pneumonia, upper respiratory tract infection, influenza, dyspnea, and blood creatinine increased.

The most common adverse reactions (≥20%) were fatigue, diarrhea, upper respiratory tract infection, muscle spasms, constipation, pyrexia, pneumonia, and dyspnea.

Table 15 summarizes the adverse reactions in patients who received DARZALEX FASPRO in PLEIADES.

Table 15: Adverse Reactions (≥10%) in Patients Who Received DARZALEX FASPRO with Lenalidomide and Dexamethasone (DARZALEX FASPRO-Rd) in PLEIADES
Adverse Reaction | DARZALEX FASPRO with Lenalidomide and Dexamethasone (N=65)
Adverse Reaction | All Grades (%) | Grades ≥3 (%)
General disorders and administration site conditions
Fatigue [Fatigue includes asthenia, and fatigue.] | 52 | 5 [Only Grade 3 adverse reactions occurred.]
Pyrexia | 23 | 2
Edema peripheral | 18 | 3
Gastrointestinal disorders
Diarrhea | 45 | 5
Constipation | 26 | 2
Nausea | 12 | 0
Vomiting | 11 | 0
Infections
Upper respiratory tract infection [Upper respiratory tract infection includes nasopharyngitis, pharyngitis, respiratory tract infection viral, rhinitis, sinusitis, upper respiratory tract infection, and upper respiratory tract infection bacterial.] | 43 | 3
Pneumonia [Pneumonia includes lower respiratory tract infection, lung infection, and pneumonia.] | 23 | 17
Bronchitis [Bronchitis includes bronchitis, and bronchitis viral.] | 14 | 2
Urinary tract infection | 11 | 0
Musculoskeletal and connective tissue disorders
Muscle spasms | 31 | 2
Back pain | 14 | 0
Respiratory, thoracic and mediastinal disorders
Dyspnea [Dyspnea includes dyspnea, and dyspnea exertional.] | 22 | 3
Cough [Cough includes cough, and productive cough.] | 14 | 0
Nervous system disorders
Peripheral sensory neuropathy | 17 | 2
Psychiatric disorders
Insomnia | 17 | 5
Metabolism and nutrition disorders
Hyperglycemia | 12 | 9
Hypocalcemia | 11 | 0

Clinically relevant adverse reactions in <10% of patients who received DARZALEX FASPRO with lenalidomide and dexamethasone included:

- Musculoskeletal and connective tissue disorders: arthralgia, musculoskeletal chest pain
- Nervous system disorders: dizziness, headache, paresthesia
- Skin and subcutaneous tissue disorders: rash, pruritus
- Gastrointestinal disorders: abdominal pain
- Infections: influenza, sepsis, herpes zoster
- Metabolism and nutrition disorders: decreased appetite
- Cardiac disorders: atrial fibrillation
- General disorders and administration site conditions: chills, infusion reaction, injection site reaction
- Vascular disorders: hypotension, hypertension

Table 16 summarizes the laboratory abnormalities in patients who received DARZALEX FASPRO in PLEIADES.

Table 16: Select Hematology Laboratory Abnormalities Worsening from Baseline in Patients Who Received DARZALEX FASPRO with Lenalidomide and Dexamethasone (DARZALEX FASPRO-Rd) in PLEIADES
Laboratory Abnormality | DARZALEX FASPRO with Lenalidomide and Dexamethasone [Denominator is based on the safety population treated with DARZALEX FASPRO-Rd (N=65).]
Laboratory Abnormality | All Grades (%) | Grades 3–4 (%)
Decreased leukocytes | 94 | 34
Decreased lymphocytes | 82 | 58
Decreased platelets | 86 | 9
Decreased neutrophils | 89 | 52
Decreased hemoglobin | 45 | 8

In Combination with Pomalidomide and Dexamethasone

The safety of DARZALEX FASPRO with pomalidomide and dexamethasone compared to pomalidomide and dexamethasone (Pd) in patients who had received at least one prior line of therapy with lenalidomide and a proteasome inhibitor (PI) was evaluated in APOLLO [see Clinical Studies (14.2)]. Patients received DARZALEX FASPRO 1,800 mg/30,000 units administered subcutaneously once weekly from weeks 1 to 8, once every 2 weeks from weeks 9 to 24 and once every 4 weeks starting with week 25 until disease progression or unacceptable toxicity in combination with pomalidomide and dexamethasone (n=149) or pomalidomide and dexamethasone (n=150). Among patients receiving DARZALEX FASPRO-Pd, 71% were exposed for 6 months or longer and 50% were exposed for greater than one year.

Serious adverse reactions occurred in 50% of patients who received DARZALEX FASPRO-Pd. The most frequent serious adverse reactions in >5% of patients who received DARZALEX FASPRO-Pd were pneumonia (15%) and lower respiratory tract infection (12%). Fatal adverse reactions occurred in 7% of patients who received DARZALEX FASPRO-Pd.

Permanent treatment discontinuation due to an adverse reaction occurred in 2% of patients who received DARZALEX FASPRO-Pd.

The most common adverse reactions (≥20%) were fatigue, pneumonia, upper respiratory tract infection, and diarrhea.

Table 17 summarizes the adverse reactions in patients who received DARZALEX FASPRO in APOLLO.

Table 17: Adverse Reactions Reported in ≥10% of Patients and With at Least a 5% Greater Frequency in the DARZALEX FASPRO-Pd Arm in APOLLO
Adverse Reaction | DARZALEX FASPRO-Pd (N=149) |  | Pd (N=150)
Adverse Reaction | All Grades (%) | Grades ≥3 (%) | All Grades (%) | Grades ≥3 (%)
General disorders and administration site conditions
Fatigue [Fatigue includes asthenia, and fatigue.] | 46 | 13 | 39 | 5 [Only Grade 3 adverse reactions occurred.]
Pyrexia | 19 | 0 | 14 | 0
Edema peripheral [Edema peripheral includes edema, edema peripheral and peripheral swelling.] | 15 | 0 | 9 | 0
Infections
Pneumonia [Pneumonia includes atypical pneumonia, lower respiratory tract infection, pneumonia, pneumonia aspiration, pneumonia bacterial, and pneumonia respiratory syncytial viral.] | 38 | 23 [Grade 5 adverse reactions occurred, n=3 (2.0%) in the DARZALEX FASPRO-Pd arm and n=2 (1.3%) in the Pd arm.] | 27 | 17
Upper respiratory infection [Upper respiratory tract infection includes nasopharyngitis, pharyngitis, respiratory syncytial virus infection, respiratory tract infection, respiratory tract infection viral, rhinitis, sinusitis, tonsillitis, upper respiratory tract infection, and viral upper respiratory tract infection.] | 36 | 1 | 22 | 2
Gastrointestinal disorders
Diarrhea | 22 | 5 | 14 | 1
Respiratory, thoracic and mediastinal disorders
Cough [Cough includes cough, and productive cough.] | 13 | 0 | 8 | 0
Key: Pd=pomalidomide-dexamethasone

Clinically relevant adverse reactions in <10% of patients who received DARZALEX FASPRO with pomalidomide and dexamethasone include:

- Metabolism and nutrition disorders: hypocalcemia, hypokalemia, decreased appetite, dehydration
- Nervous system disorders: peripheral sensory neuropathy, syncope, headache, paresthesia, dizziness
- Musculoskeletal and connective tissue disorders: muscle spasms, musculoskeletal chest pain, arthralgia
- Psychiatric disorders: insomnia
- Gastrointestinal disorders: nausea, abdominal pain, vomiting
- Skin and subcutaneous tissue disorders: rash, pruritus
- Cardiac disorders: atrial fibrillation
- General disorders and administration site conditions: infusion reactions, chills, injection site reaction
- Infections: urinary tract infection, influenza, hepatitis B reactivation, herpes zoster, sepsis
- Vascular disorders: hypertension, hypotension

Table 18 summarizes the laboratory abnormalities in patients who received DARZALEX FASPRO in APOLLO.

Table 18: Select Hematology Laboratory Abnormalities Worsening from Baseline in Patients Who Received DARZALEX FASPRO-Pd or Pd in APOLLO
Laboratory Abnormality | DARZALEX FASPRO-Pd [Denominator is based on number of subjects with a baseline and post-baseline laboratory value for each laboratory test: N=148 for DARZALEX FASPRO-Pd and N=149 for Pd.] |  | Pd
Laboratory Abnormality | All Grades (%) | Grades 3–4 (%) | All Grades (%) | Grades 3–4 (%)
Decreased neutrophils | 97 | 84 | 84 | 63
Decreased leukocytes | 95 | 64 | 82 | 40
Decreased lymphocytes | 93 | 59 | 79 | 33
Decreased platelets | 75 | 19 | 60 | 19
Decreased hemoglobin | 51 | 16 | 57 | 15
Key: Pd=pomalidomide-dexamethasone

In Combination with Carfilzomib and Dexamethasone

The safety of DARZALEX FASPRO with carfilzomib and dexamethasone was evaluated in a single-arm cohort of PLEIADES [see Clinical Studies (14.2)]. Patients received DARZALEX FASPRO 1,800 mg/30,000 units administered subcutaneously once weekly from Weeks 1 to 8, once every 2 weeks from Weeks 9 to 24 and once every 4 weeks starting with Week 25 until disease progression or unacceptable toxicity (N=66) in combination with carfilzomib and dexamethasone. Among these patients, 77% were exposed for 6 months or longer and 27% were exposed for greater than one year.

Serious adverse reactions occurred in 27% of patients who received DARZALEX FASPRO in combination with carfilzomib and dexamethasone. Fatal adverse reactions occurred in 3% of patients who received DARZALEX FASPRO in combination with carfilzomib and dexamethasone.

Permanent discontinuation of DARZALEX FASPRO due to an adverse reaction occurred in 6% of patients who received DARZALEX FASPRO.

Dosage interruptions due to an adverse reaction occurred in 46% of patients who received DARZALEX FASPRO.

The most common adverse reactions (≥20%) were upper respiratory tract infection, fatigue, insomnia, hypertension, diarrhea, cough, dyspnea, headache, pyrexia, nausea, and edema peripheral.

Table 19 summarizes the adverse reactions in patients who received DARZALEX FASPRO with carfilzomib and dexamethasone (DARZALEX FASPRO-Kd) in PLEIADES.

Table 19: Adverse Reactions (≥10%) in Patients Who Received DARZALEX FASPRO with Carfilzomib and Dexamethasone (DARZALEX FASPRO-Kd) in PLEIADES
Adverse Reaction | DARZALEX FASPRO-Kd (N=66)
Adverse Reaction | All Grades (%) | Grade ≥3 (%)
Infections and infestations
Upper respiratory tract infection [Upper respiratory tract infection includes nasopharyngitis, pharyngitis, respiratory tract infection, respiratory tract infection viral, rhinitis, sinusitis, tonsillitis, upper respiratory tract infection, viral pharyngitis, and viral upper respiratory tract infection.] | 52 | 0
Bronchitis [Bronchitis includes bronchitis, and bronchitis viral.] | 12 | 2 [Only Grade 3 adverse reactions occurred.]
General disorders and administration site conditions
Fatigue [Fatigue includes asthenia, and fatigue.] | 39 | 2
Pyrexia | 21 | 2
Edema peripheral [Edema peripheral includes generalized edema, edema peripheral, and peripheral swelling.] | 20 | 0
Psychiatric disorders
Insomnia | 33 | 6
Vascular disorders
Hypertension [Hypertension includes blood pressure increased, and hypertension.] | 32 | 21
Gastrointestinal disorders
Diarrhea | 29 | 0
Nausea | 21 | 0
Vomiting | 15 | 0
Respiratory, thoracic and mediastinal disorders
Cough [Cough includes cough, and productive cough.] | 24 | 0
Dyspnea [Dyspnea includes dyspnea, and dyspnea exertional.] | 23 | 2
Nervous system disorders
Headache | 23 | 0
Peripheral sensory neuropathy | 11 | 0
Musculoskeletal and connective tissue disorders
Back pain | 17 | 2
Musculoskeletal chest pain | 11 | 0

Clinically relevant adverse reactions in <10% of patients who received DARZALEX FASPRO with carfilzomib and dexamethasone include:

- Gastrointestinal disorders: abdominal pain, constipation, pancreatitis
- Infection and infestations: pneumonia, influenza, urinary tract infection, herpes zoster, sepsis
- Metabolism and nutrition disorders: hyperglycemia, decreased appetite, hypocalcemia
- Musculoskeletal and connective tissue disorders: muscle spasms, arthralgia
- Nervous system disorders: paresthesia, dizziness, syncope
- General disorders and administration site conditions: injection site reaction, infusion reactions, chills
- Skin and subcutaneous tissue disorders: rash, pruritus
- Cardiac disorders: cardiac failure
- Vascular disorders: hypotension

Table 20 summarizes the laboratory abnormalities in patients who received DARZALEX FASPRO with carfilzomib and dexamethasone in PLEIADES.

Table 20: Select Laboratory Abnormalities (≥30%) Worsening from Baseline in Patients Who Received DARZALEX FASPRO-Kd in PLEIADES
Laboratory Abnormality | DARZALEX FASPRO-Kd [Denominator is based on the safety population treated with DARZALEX FASPRO-Kd (N=66).]
Laboratory Abnormality | All Grades (%) | Grades 3–4 (%)
Decreased platelets | 88 | 18
Decreased lymphocytes | 83 | 50
Decreased leukocytes | 68 | 18
Decreased neutrophils | 55 | 15
Decreased hemoglobin | 47 | 6
Decreased corrected calcium | 45 | 2
Increased alanine aminotransferase (ALT) | 35 | 5

Monotherapy

The safety of DARZALEX FASPRO as monotherapy was evaluated in COLUMBA [see Clinical Studies (14.2)]. Patients received DARZALEX FASPRO 1,800 mg/30,000 units administered subcutaneously or daratumumab 16 mg/kg administered intravenously; each administered once weekly from weeks 1 to 8, once every 2 weeks from weeks 9 to 24 and once every 4 weeks starting with week 25 until disease progression or unacceptable toxicity. Among patients receiving DARZALEX FASPRO, 37% were exposed for 6 months or longer and 1% were exposed for greater than one year.

Serious adverse reactions occurred in 26% of patients who received DARZALEX FASPRO. Fatal adverse reactions occurred in 5% of patients. Fatal adverse reactions occurring in more than 1 patient were general physical health deterioration, septic shock, and respiratory failure.

Permanent discontinuation due to an adverse reaction occurred in 10% of patients who received DARZALEX FASPRO. Adverse reactions resulting in permanent discontinuation of DARZALEX FASPRO in more than 2 patients were thrombocytopenia and hypercalcemia.

Dosage interruptions due to an adverse reaction occurred in 26% of patients who received DARZALEX FASPRO. Adverse reactions requiring dosage interruption in >5% of patients included thrombocytopenia.

The most common adverse reaction (≥20%) was upper respiratory tract infection.

Table 21 summarizes the adverse reactions in COLUMBA.

Table 21: Adverse Reactions (≥10%) in Patients Who Received DARZALEX FASPRO or Intravenous Daratumumab in COLUMBA
Adverse Reaction | DARZALEX FASPRO (N=260) |  | Intravenous Daratumumab (N=258)
Adverse Reaction | All Grades (%) | Grade ≥3 (%) | All Grades (%) | Grade ≥3 (%)
Infections
Upper respiratory tract infection [Upper respiratory tract infection includes acute sinusitis, nasopharyngitis, pharyngitis, respiratory syncytial virus infection, respiratory tract infection, rhinitis, rhinovirus infection, sinusitis, and upper respiratory tract infection.] | 24 | 1 [Only Grade 3 adverse reactions occurred.] | 22 | 1
Pneumonia [Pneumonia includes lower respiratory tract infection, lung infection, pneumocystis jirovecii pneumonia, and pneumonia.] | 8 | 5 | 10 | 6 [Grade 5 adverse reactions occurred.]
Gastrointestinal disorders
Diarrhea | 15 | 1 | 11 | 0.4
Nausea | 8 | 0.4 | 11 | 0.4
General disorders and administration site conditions
Fatigue [Fatigue includes asthenia, and fatigue.] | 15 | 1 | 16 | 2
Infusion reactions [Infusion reactions includes terms determined by investigators to be related to infusion.] | 13 | 2 | 34 | 5
Pyrexia | 13 | 0 | 13 | 1
Chills | 6 | 0.4 | 12 | 1
Musculoskeletal and connective tissue disorders
Back pain | 10 | 2 | 12 | 3
Respiratory, thoracic and mediastinal disorders
Cough [Cough includes cough, and productive cough.] | 9 | 1 | 14 | 0
Dyspnea [Dyspnea includes dyspnea, and dyspnea exertional.] | 6 | 1 | 11 | 1

Clinically relevant adverse reactions in <10% of patients who received DARZALEX FASPRO included:

- General disorders and administration site conditions: injection site reaction, peripheral edema
- Musculoskeletal and connective tissue disorders: arthralgia, musculoskeletal chest pain, muscle spasms
- Gastrointestinal disorders: constipation, vomiting, abdominal pain
- Metabolism and nutrition disorders: decreased appetite, hyperglycemia, hypocalcemia, dehydration
- Psychiatric disorders: insomnia
- Vascular disorders: hypertension, hypotension
- Nervous system disorders: dizziness, peripheral sensory neuropathy, paresthesia
- Infections: bronchitis, influenza, urinary tract infection, herpes zoster, sepsis, hepatitis B virus reactivation
- Skin and subcutaneous tissue disorders: pruritus, rash
- Cardiac disorders: atrial fibrillation
- Respiratory, thoracic and mediastinal disorders: pulmonary edema

Table 22 summarizes the laboratory abnormalities in COLUMBA.

Table 22: Select Hematology Laboratory Abnormalities Worsening from Baseline in Patients Receiving DARZALEX FASPRO or Intravenous Daratumumab in COLUMBA
Laboratory Abnormality | DARZALEX FASPRO [Denominator is based on the safety population treated with DARZALEX FASPRO (N=260) and Intravenous Daratumumab (N=258).] |  | Intravenous Daratumumab
Laboratory Abnormality | All Grades (%) | Grades 3–4 (%) | All Grades (%) | Grades 3–4 (%)
Decreased leukocytes | 65 | 19 | 57 | 14
Decreased lymphocytes | 59 | 36 | 56 | 36
Decreased neutrophils | 55 | 19 | 43 | 11
Decreased platelets | 43 | 16 | 45 | 14
Decreased hemoglobin | 42 | 14 | 39 | 16

High-Risk Smoldering Multiple Myeloma

The safety of DARZALEX FASPRO as monotherapy in patients with high-risk smoldering multiple myeloma was evaluated in AQUILA [see Clinical Studies (14.3)]. Patients received DARZALEX FASPRO 1,800 mg/30,000 units administered subcutaneously once weekly from weeks 1 to 8, once every 2 weeks from weeks 9 to 24 and once every 4 weeks starting with week 25 until 39 cycles or up to 36 months or until diagnosis of multiple myeloma or unacceptable toxicity.

The median duration of treatment for patients receiving DARZALEX FASPRO was 35 months (0 to 36 months).

Serious adverse reactions occurred in 29% of patients who received DARZALEX FASPRO. The most frequent serious adverse reactions in ≥2% of patients who received DARZALEX FASPRO were pneumonia (7%), fracture (3%), sepsis (2%), and upper respiratory tract infection (2%). Fatal adverse reactions occurred in 1% of patients who received DARZALEX FASPRO, including COVID-19 (0.5%) and pneumonia (0.5%).

Permanent treatment discontinuation due to an adverse reaction occurred in 6% of patients who received DARZALEX FASPRO. Adverse reactions which resulted in permanent discontinuation of DARZALEX FASPRO in more than 1 patient included fatigue, anxiety, and dyspnea.

Dosage interruptions of DARZALEX FASPRO due to an adverse reaction occurred in 47% of patients. Adverse reactions which required dosage interruption in ≥5% of patients included upper respiratory infection, pneumonia, and COVID-19.

The most common adverse reactions (≥20%) were upper respiratory tract infection, musculoskeletal pain, fatigue, diarrhea, rash, sleep disorder, sensory neuropathy, and injection site reactions.

Table 23 summarizes the adverse reactions in patients who received DARZALEX FASPRO in AQUILA.

Table 23: Adverse Reactions Reported in ≥10% of Patients with High-Risk Smoldering Multiple Myeloma and with at Least a 5% Greater Frequency in the DARZALEX FASPRO Arm in AQUILA
 | DARZALEX FASPRO (N=193) |  | ACTM (N=196)
Adverse Reaction | All Grades (%) | Grade 3 or 4 (%) | All Grades (%) | Grade 3 or 4 (%)
Infections
Upper respiratory tract infection [Upper respiratory tract infection includes acute sinusitis, adenoviral upper respiratory infection, catarrh, influenza, influenza like illness, laryngitis, metapneumovirus infection, nasal congestion, nasopharyngitis, parainfluenzae virus infection, pharyngitis, respiratory tract congestion, respiratory tract infection, respiratory tract infection viral, sinus congestion, sinusitis, throat irritation, tonsillitis, tracheitis, upper respiratory tract congestion, upper respiratory tract infection, upper respiratory tract infection bacterial, upper-airway cough syndrome, and viral upper respiratory tract infection.] | 66 | 1 [Only Grade 3 adverse reactions occurred.] | 27 | 0
Pneumonia [Pneumonia includes covid-19 pneumonia, lower respiratory tract infection, organizing pneumonia, pneumonia, pneumonia bacterial, pneumonia pneumococcal, pneumonia streptococcal, and pneumonia viral.] | 16 | 7 [Fatal adverse reactions occurred for Pneumonia: n=1 (1%) in the DARZALEX FASPRO arm.] | 8 | 3
Rhinitis [Rhinitis includes rhinitis, rhinitis atrophic, rhinorrhea, rhinovirus infection, and viral rhinitis.] | 10 | 0 | 2 | 0
Musculoskeletal and connective tissue disorders
Musculoskeletal pain [Musculoskeletal pain includes arthralgia, axillary pain, back pain, breast pain, chest pain, facial spasm, fibromyalgia, flank pain, groin pain, muscle fatigue, muscle rupture, muscle spasms, muscle strain, muscle tightness, muscular weakness, musculoskeletal chest pain, musculoskeletal pain, musculoskeletal stiffness, myalgia, neck pain, non-cardiac chest pain, pain, pain in extremity, pain in jaw, periarthritis, radicular pain, rotator cuff syndrome, spinal pain, spinal stenosis, and tendon pain.] | 59 | 1 | 42 | 3
General disorders and administration site conditions
Fatigue [Fatigue includes asthenia, fatigue, and malaise.] | 42 | 3 | 21 | 1
Injection site reactions [Injection site reaction includes injection site discoloration, injection site erythema, injection site hemorrhage, injection site induration, injection site edema, injection site pain, injection site pruritus, injection site rash, injection site swelling, injection site urticaria, injection site vesicles, and injection site warmth.] | 20 | 0 | 0 | 0
Infusion-related reactions [Infusion-related reactions includes terms determined by investigators to be related to infusion.] | 17 | 1 | 0 | 0
Pyrexia | 17 | 0 | 3 | 1
Edema [Edema includes brain edema, eye swelling, eyelid edema, generalized edema, joint swelling, laryngeal edema, localized edema, edema, edema peripheral, peripheral swelling, post procedural edema, post procedural swelling, swelling face, and swelling of eyelid.] | 15 | 1 | 5 | 1
Gastrointestinal disorders
Diarrhea | 27 | 2 | 5 | 1
Nausea | 19 | 0 | 5 | 0
Abdominal pain [Abdominal pain includes abdominal discomfort, abdominal pain, abdominal pain lower, abdominal pain upper, abdominal tenderness, epigastric discomfort, and gastrointestinal pain.] | 17 | 1 | 7 | 2
Skin and subcutaneous tissue disorders
Rash [Rash includes acne, dermatitis, dermatitis allergic, dermatitis bullous, dermatitis contact, drug eruption, drug hypersensitivity, eczema, eczema asteatotic, eczema infected, erysipelas, erythema, erythema multiforme, rash, rash erythematous, rash maculo-papular, rash papular, rash pruritic, seborrheic dermatitis, seborrheic keratosis, skin lesion, skin reaction, skin ulcer, and urticaria.] | 27 | 1 | 6 | 1
Psychiatric disorders
Sleep disorder [Sleep disorder includes insomnia, restless legs syndrome, sleep apnea syndrome, sleep deficit, and sleep disorder.] | 24 | 1 | 5 | 0
Nervous system disorders
Sensory neuropathy [Sensory neuropathy includes allodynia, anosmia, burning sensation, carpal tunnel syndrome, cervical radiculopathy, cervicobrachial syndrome, dysesthesia, hypoesthesia, hypoesthesia oral, paresthesia, paresthesia oral, peripheral sensorimotor neuropathy, peripheral sensory neuropathy, pharyngeal paresthesia, polyneuropathy, and sensory disturbance.] | 20 | 0 | 8 | 0
Headache [Headache includes headache, migraine, and vascular headache.] | 18 | 1 | 8 | 0
Dizziness [Dizziness includes dizziness, and dizziness postural.] | 12 | 0 | 5 | 0
Respiratory, thoracic and mediastinal disorders
Cough [Cough includes cough, and productive cough.] | 19 | 0 | 7 | 0
Dyspnea [Dyspnea includes dyspnea, and dyspnea exertional.] | 18 | 1 | 6 | 1
Key: ACTM=active monitoring

Clinically relevant adverse reactions in <10% of patients who received DARZALEX FASPRO included:

- Gastrointestinal disorders: constipation, vomiting
- Skin and subcutaneous tissue disorders: pruritus
- Infections: bronchitis, urinary tract infection, herpes zoster, sepsis
- General disorders and administration site conditions: chills
- Metabolism and nutrition disorders: decreased appetite, hyperglycemia, dehydration
- Nervous system disorders: syncope
- Vascular disorders: hypotension

Table 24 summarizes the laboratory abnormalities in patients who received DARZALEX FASPRO in AQUILA.

Table 24: Select Laboratory Abnormalities (≥20%) that Worsened from Baseline in Patients with High-Risk Smoldering Multiple Myeloma Who Received DARZALEX FASPRO in AQUILA
 | DARZALEX FASPRO [Denominator is based on number of subjects with a baseline and post-baseline laboratory value for each laboratory test: N=191 for DARZALEX FASPRO and N=191 for ACTM.] |  | ACTM
Laboratory Abnormality | All Grades (%) | Grade 3 or 4 (%) | All Grades (%) | Grade 3 or 4 (%)
Hematology
Decreased lymphocytes | 47 | 6 | 12 | 3
Decreased hemoglobin | 42 | 0 | 44 | 2
Decreased leukocytes | 34 | 3 | 27 | 2
Decreased neutrophils | 34 | 6 | 29 | 4
Decreased platelets | 19 | 1 | 9 | 1
Chemistry
Decreased albumin | 28 | 0 | 15 | 1
Increased alanine aminotransferase (ALT) | 25 | 1 | 13 | 1
Decreased sodium | 24 | 3 | 19 | 2
Increased creatinine | 20 | 0 | 13 | 1
Increased aspartate aminotransferase (AST) | 20 | 0 | 12 | 1
Key: ACTM=active monitoring

Light Chain Amyloidosis

In Combination with Bortezomib, Cyclophosphamide and Dexamethasone

The safety of DARZALEX FASPRO with bortezomib, cyclophosphamide and dexamethasone (DARZALEX FASPRO-VCd) was evaluated in ANDROMEDA [see Clinical Studies (14.4)]. Patients received DARZALEX FASPRO 1,800 mg/30,000 units administered subcutaneously once weekly from weeks 1 to 8, once every 2 weeks from weeks 9 to 24 and once every 4 weeks starting with week 25 until disease progression or unacceptable toxicity or a maximum of 2 years. Among patients who received DARZALEX FASPRO-VCd, 74% were exposed for 6 months or longer and 32% were exposed for greater than one year.

Serious adverse reactions occurred in 43% of patients who received DARZALEX FASPRO in combination with VCd. Serious adverse reactions that occurred in at least 5% of patients in the DARZALEX FASPRO-VCd arm were pneumonia (9%), cardiac failure (8%), and sepsis (5%). Fatal adverse reactions occurred in 11% of patients. Fatal adverse reactions that occurred in more than one patient included cardiac arrest (4%), sudden death (3%), cardiac failure (3%), and sepsis (1%).

Permanent discontinuation of DARZALEX FASPRO due to an adverse reaction occurred in 5% of patients. Adverse reactions resulting in permanent discontinuation of DARZALEX FASPRO in more than one patient were pneumonia, sepsis, and cardiac failure.

Dosage interruptions (defined as dose delays or skipped doses) due to an adverse reaction occurred in 36% of patients who received DARZALEX FASPRO. Adverse reactions which required a dosage interruption in ≥3% of patients included upper respiratory tract infection (9%), pneumonia (6%), cardiac failure (4%), fatigue (3%), herpes zoster (3%), dyspnea (3%), and neutropenia (3%).

The most common adverse reactions (≥20%) were upper respiratory tract infection, diarrhea, peripheral edema, constipation, fatigue, peripheral sensory neuropathy, nausea, insomnia, dyspnea, and cough.

Table 25 below summarizes the adverse reactions in patients who received DARZALEX FASPRO in ANDROMEDA.

Table 25: Adverse Reactions (≥10%) in Patients with AL Amyloidosis Who Received DARZALEX FASPRO with Bortezomib, Cyclophosphamide and Dexamethasone (DARZALEX FASPRO-VCd) with a Difference Between Arms of >5% Compared to VCd in ANDROMEDA
Adverse Reaction | DARZALEX FASPRO-VCd (N=193) |  | VCd (N=188)
Adverse Reaction | All Grades (%) | Grades 3–4 (%) | All Grades (%) | Grades 3–4 (%)
Infections
Upper respiratory tract infection [Upper respiratory tract infection includes laryngitis, nasopharyngitis, pharyngitis, respiratory syncytial virus infection, respiratory tract infection, respiratory tract infection viral, rhinitis, rhinovirus infection, sinusitis, tonsillitis, tracheitis, upper respiratory tract infection, upper respiratory tract infection bacterial, and viral upper respiratory tract infection.] | 40 | 1 [Only Grade 3 adverse reactions occurred.] | 21 | 1
Pneumonia [Pneumonia includes lower respiratory tract infection, pneumonia, pneumonia aspiration, and pneumonia pneumococcal.] | 15 | 10 | 9 | 5
Gastrointestinal disorders
Diarrhea | 36 | 6 | 30 | 4
Constipation | 34 | 2 | 29 | 0
Nervous system disorders
Peripheral sensory neuropathy | 31 | 3 | 20 | 2
Respiratory, thoracic and mediastinal disorders
Dyspnea [Dyspnea includes dyspnea, and dyspnea exertional.] | 26 | 4 | 20 | 4
Cough [Cough includes cough, and productive cough.] | 20 | 1 | 11 | 0
Musculoskeletal and connective tissue disorders
Back pain | 12 | 2 | 6 | 0
Arthralgia | 10 | 0 | 5 | 0
Muscle spasms | 10 | 1 | 5 | 0
Cardiac disorders
Arrhythmia [Arrhythmia includes atrial flutter, atrial fibrillation, supraventricular tachycardia, bradycardia, arrhythmia, bradyarrhythmia, cardiac flutter, extrasystoles, supraventricular extrasystoles, ventricular arrhythmia, ventricular extrasystoles, atrial tachycardia, ventricular tachycardia] | 11 | 4 | 5 | 2
General disorders and administration site conditions
Injection site reactions [Injection site reactions includes terms determined by investigators to be related to daratumumab injection.] | 11 | 0 | 0 | 0

Clinically relevant adverse reactions not included in Table 25 and occurred in patients who received DARZALEX FASPRO with bortezomib, cyclophosphamide and dexamethasone included:

- Skin and subcutaneous tissue disorders: rash, pruritus
- Nervous system disorders: paresthesia
- General disorders and administration site conditions: infusion reaction, chills
- Cardiac disorders: cardiac failure [Cardiac failure includes cardiac dysfunction, cardiac failure, cardiac failure congestive, cardiovascular insufficiency, diastolic dysfunction, pulmonary edema, and left ventricular dysfunction occurred in 11% of patients.] , cardiac arrest
- Metabolism and nutrition disorders: hyperglycemia, hypocalcemia, dehydration
- Infections: bronchitis, herpes zoster, sepsis, urinary tract infection, influenza
- Vascular disorders: hypertension
- Musculoskeletal and connective tissue disorders: musculoskeletal chest pain
- Gastrointestinal disorders: pancreatitis
- Respiratory, thoracic and mediastinal disorders: pulmonary edema

Table 26 summarizes the laboratory abnormalities in patients who received DARZALEX FASPRO in ANDROMEDA.

Table 26: Select Hematology Laboratory Abnormalities Worsening from Baseline in Patients Who Received DARZALEX FASPRO with Bortezomib, Cyclophosphamide and Dexamethasone (DARZALEX FASPRO-VCd) in ANDROMEDA
Laboratory Abnormality | DARZALEX FASPRO-VCd |  | VCd
Laboratory Abnormality | All Grades (%) | Grades 3–4 (%) | All Grades (%) | Grades 3–4 (%)
Decreased lymphocytes | 81 | 54 | 71 | 46
Decreased hemoglobin | 66 | 6 | 70 | 6
Decreased leukocytes | 60 | 7 | 46 | 4
Decreased platelets | 46 | 3 | 40 | 4
Decreased neutrophils | 30 | 6 | 18 | 4
Denominator is based on the number of patients with a baseline and post-baseline laboratory value for each laboratory test, N=188 for DARZALEX FASPRO-VCd and N=186 for VCd.

Cardiac Adverse Reactions in Light Chain (AL) Amyloidosis

Among patients who received DARZALEX FASPRO in combination with VCd, 72% of patients had baseline cardiac involvement with Mayo Cardiac Stage I (3%), Stage II (46%) and Stage III (51%). Serious cardiac disorders occurred in 16% of patients (8% of patients with Mayo Cardiac Stage I and II and 28% of patients with Stage III). Serious cardiac disorders in >2% of patients included cardiac failure (8%), cardiac arrest (4%) and arrhythmia (4%). Fatal cardiac disorders occurred in 10% of patients (5% of patients with Mayo Cardiac Stage I and II and 19% of patients with Stage III) who received DARZALEX FASPRO in combination with VCd. Fatal cardiac disorders that occurred in more than one patient in the DARZALEX FASPRO-VCd arm included cardiac arrest (4%), sudden death (3%), and cardiac failure (3%).

6.2 Postmarketing Experience

The following adverse reactions have been identified with post-approval use of daratumumab. Because these reactions are reported voluntarily from a population of uncertain size, it is not always possible to reliably estimate their frequency or establish a causal relationship to drug exposure.

Immune System: Anaphylactic reaction, Systemic administration reactions (including death)

Gastrointestinal: Pancreatitis

Infections: Cytomegalovirus, Listeriosis

7 DRUG INTERACTIONS

7.1 Effects of Daratumumab on Laboratory Tests

Interference with Indirect Antiglobulin Tests (Indirect Coombs Test)

Daratumumab binds to CD38 on RBCs and interferes with compatibility testing, including antibody screening and cross matching. Daratumumab interference mitigation methods include treating reagent RBCs with dithiothreitol (DTT) to disrupt daratumumab binding [see References (15)] or genotyping. Since the Kell blood group system is also sensitive to DTT treatment, supply K-negative units after ruling out or identifying alloantibodies using DTT-treated RBCs.

If an emergency transfusion is required, administer non-cross-matched ABO/RhD-compatible RBCs per local blood bank practices.

Interference with Serum Protein Electrophoresis and Immunofixation Tests

Daratumumab may be detected on serum protein electrophoresis (SPE) and immunofixation (IFE) assays used for monitoring disease monoclonal immunoglobulins (M protein). False positive SPE and IFE assay results may occur for patients with IgG kappa myeloma protein impacting initial assessment of complete responses by International Myeloma Working Group (IMWG) criteria. In DARZALEX FASPRO-treated patients with persistent very good partial response, where daratumumab interference is suspected, consider using a FDA-approved daratumumab-specific IFE assay to distinguish daratumumab from any remaining endogenous M protein in the patient's serum, to facilitate determination of a complete response.

8 USE IN SPECIFIC POPULATIONS

8.1 Pregnancy

Risk Summary

DARZALEX FASPRO can cause fetal harm when administered to a pregnant woman. The assessment of associated risks with daratumumab products is based on the mechanism of action and data from target antigen CD38 knockout animal models (see Data). There are no available data on the use of DARZALEX FASPRO in pregnant women to evaluate drug-associated risk of major birth defects, miscarriage or adverse maternal or fetal outcomes. Animal reproduction studies have not been conducted.

In the U.S. general population, the estimated background risk of major birth defects and miscarriage in clinically recognized pregnancies is 2% to 4% and 15% to 20%, respectively.

The combination of DARZALEX FASPRO and lenalidomide, thalidomide or pomalidomide is contraindicated in pregnant women, because lenalidomide, thalidomide and pomalidomide may cause birth defects and death of the unborn child. Lenalidomide, thalidomide and pomalidomide are only available through a REMS program. Refer to the lenalidomide, thalidomide or pomalidomide prescribing information on use during pregnancy.

Clinical Considerations

Fetal/Neonatal Adverse Reactions

Immunoglobulin G1 (IgG1) monoclonal antibodies are transferred across the placenta. Based on its mechanism of action, DARZALEX FASPRO may cause depletion of fetal CD38 positive immune cells and decreased bone density. Defer administering live vaccines to neonates and infants exposed to daratumumab in utero until a hematology evaluation is completed.

Data

Animal Data

DARZALEX FASPRO for subcutaneous injection contains daratumumab and hyaluronidase. Mice that were genetically modified to eliminate all CD38 expression (CD38 knockout mice) had reduced bone density at birth that recovered by 5 months of age. Data from studies using CD38 knockout animal models also suggest the involvement of CD38 in the regulation of humoral immune responses (mice), feto-maternal immune tolerance (mice), and early embryonic development (frogs).

No systemic exposure of hyaluronidase was detected in monkeys given 220,000 U/kg subcutaneously (440 times higher than the human dose) and there were no effects on embryo-fetal development in pregnant mice given 360,000 U/kg hyaluronidase subcutaneously daily during organogenesis, which is 720 times higher than the human dose.

There were no effects on pre- and post-natal development through sexual maturity in offspring of mice treated daily from implantation through lactation with 1,100,000 U/kg hyaluronidase subcutaneously, which is 2,200 times higher than the human doses.

8.2 Lactation

Risk Summary

There is no data on the presence of daratumumab and hyaluronidase in human milk, the effects on the breastfed child, or the effects on milk production. Maternal immunoglobulin G is known to be present in human milk. Published data suggest that antibodies in breast milk do not enter the neonatal and infant circulations in substantial amounts. Because of the potential for serious adverse reactions in the breastfed child when DARZALEX FASPRO is administered with lenalidomide, thalidomide or pomalidomide, advise women not to breastfeed during treatment with DARZALEX FASPRO. Refer to lenalidomide, thalidomide or pomalidomide prescribing information for additional information.

Data

Animal Data

No systemic exposure of hyaluronidase was detected in monkeys given 220,000 U/kg subcutaneously (440 times higher than the human dose) and there were no effects on post-natal development through sexual maturity in offspring of mice treated daily during lactation with 1,100,000 U/kg hyaluronidase subcutaneously, which is 2,200 times higher than the human doses.

8.3 Females and Males of Reproductive Potential

DARZALEX FASPRO can cause fetal harm when administered to a pregnant woman [see Use in Specific Populations (8.1)].

Pregnancy Testing

With the combination of DARZALEX FASPRO with lenalidomide, thalidomide or pomalidomide, refer to the lenalidomide, thalidomide or pomalidomide labeling for pregnancy testing requirements prior to initiating treatment in females of reproductive potential.

Contraception

Advise females of reproductive potential to use effective contraception during treatment with DARZALEX FASPRO and for 3 months after the last dose. Additionally, refer to the lenalidomide, thalidomide or pomalidomide labeling for additional recommendations for contraception.

8.4 Pediatric Use

Safety and effectiveness of DARZALEX FASPRO in pediatric patients have not been established.

8.5 Geriatric Use

Of the 291 patients who received DARZALEX FASPRO as monotherapy for relapsed and refractory multiple myeloma, 37% were 65 to <75 years of age, and 19% were 75 years of age and older. No overall differences in effectiveness of DARZALEX FASPRO have been observed between patients ≥65 years of age and younger patients. Adverse reactions that occurred at a higher frequency (≥5% difference) in patients ≥65 years of age included upper respiratory tract infection, urinary tract infection, dizziness, cough, dyspnea, diarrhea, nausea, fatigue, and peripheral edema. Serious adverse reactions that occurred at a higher frequency (≥2% difference) in patients ≥65 years of age included pneumonia.

Of the 214 patients who received DARZALEX FASPRO as combination therapy with pomalidomide and dexamethasone or DARZALEX FASPRO as combination therapy with lenalidomide and low-dose dexamethasone for relapsed and refractory multiple myeloma, 43% were 65 to <75 years of age, and 18% were 75 years of age and older. No overall differences in effectiveness were observed between patients ≥65 years (n=131) and <65 years (n=85). Adverse reactions occurring at a higher frequency (≥5% difference) in patients ≥65 years of age included fatigue, pyrexia, peripheral edema, urinary tract infection, diarrhea, constipation, vomiting, dyspnea, cough, and hyperglycemia. Serious adverse reactions occurring at a higher frequency (≥2% difference) in patients ≥65 years of age included neutropenia, thrombocytopenia, diarrhea, anemia, COVID-19, ischemic colitis, deep vein thrombosis, general physical health deterioration, pulmonary embolism, and urinary tract infection.

Of the 355 patients who were newly diagnosed with multiple myeloma and eligible for ASCT who received DARZALEX FASPRO as combination therapy with bortezomib, lenalidomide and dexamethasone during induction and consolidation in the clinical trial, 74% were <65 years of age, and 26% were 65 to 70 years of age. The clinical trial did not enroll patients older than 70 years of age [see Clinical Studies (14.1)]. No overall differences in effectiveness of DARZALEX FASPRO in combination with bortezomib, lenalidomide and dexamethasone were observed between patients <65 years of age compared to patients 65 to 70 years of age. Adverse reactions that occurred at a higher frequency (≥5% difference) in patients 65 to 70 years of age included constipation, hemorrhoids, nausea, injection site erythema, bronchitis, nasopharyngitis, back pain, myalgia, pain in extremity, dysgeusia, peripheral motor neuropathy, and insomnia. Serious adverse reactions that occurred at a higher frequency (≥2% difference) in patients 65 to 70 years of age included febrile bone marrow aplasia, atrial fibrillation, pyrexia, and orthostatic hypotension.

Of the 197 patients with newly diagnosed multiple myeloma in CEPHEUS who received DARZALEX FASPRO as combination therapy with bortezomib, lenalidomide and dexamethasone, 61% were 65 to <75 years of age, and 21% were 75 years of age and older. The clinical trial did not enroll patients over age 80 [see Clinical Studies (14.1)]. No overall differences in effectiveness of DARZALEX FASPRO in combination with bortezomib, lenalidomide and dexamethasone were observed between younger patients and patients ≥75 years. Adverse reactions occurring at a higher frequency (≥5% difference) in patients ≥75 years of age included sensory neuropathy, diarrhea, fatigue, constipation, renal impairment, dizziness, pyrexia, rash, dyspnea, fracture, arrhythmia, decreased appetite, urinary tract infection, injection site reaction, encephalopathy, vomiting, taste disorder, and herpes. Serious adverse reactions occurring at a higher frequency (≥5% difference) in patients ≥75 years of age included urinary tract infection, upper respiratory tract infection, diarrhea, and encephalopathy.

Of the 193 patients who received DARZALEX FASPRO as monotherapy for high-risk smoldering multiple myeloma, 35% (n=67) were 65 to <75 years of age, and 11% (n=21) were 75 years of age and older. No overall difference in effectiveness were observed between patients 65 to 75 years (n=67) and <65 years (n=105); there were too few patients 75 years of age and older to assess for a difference in effectiveness. Adverse reactions that occurred at a higher frequency (≥5% difference) in patients ≥65 years of age were pneumonia, dizziness, arrhythmia, hemorrhage, arthritis, and cataract. Serious adverse reactions occurring at a higher frequency (≥5% difference) in patients ≥65 years of age included pneumonia and fracture.

Of the 193 patients who received DARZALEX FASPRO as part of a combination therapy for light chain (AL) amyloidosis, 35% were 65 to <75 years of age, and 10% were 75 years of age and older. Clinical studies of DARZALEX FASPRO as part of a combination therapy for patients with light chain (AL) amyloidosis did not include sufficient numbers of patients aged 65 and older to determine whether effectiveness differs from that of younger patients. Adverse reactions that occurred at a higher frequency in patients ≥65 years of age were peripheral edema, asthenia, pneumonia and hypotension.

No clinically meaningful differences in the pharmacokinetics of daratumumab were observed in geriatric patients compared to younger adult patients [see Clinical Pharmacology (12.3)].

11 DESCRIPTION

Daratumumab is an immunoglobulin G1 kappa (IgG1κ) human monoclonal antibody that binds to the CD38 antigen. Daratumumab is produced in Chinese Hamster Ovary (CHO) cells using recombinant DNA technology. The molecular weight of daratumumab is approximately 148 kDa.

Hyaluronidase (recombinant human) is an endoglycosidase used to increase the dispersion and absorption of co-administered drugs when administered subcutaneously. It is a glycosylated single-chain protein produced by Chinese Hamster Ovary cells containing a DNA plasmid encoding for a soluble fragment of human hyaluronidase (PH20). Hyaluronidase (recombinant human) has a molecular weight of approximately 61 kDa.

DARZALEX FASPRO® (daratumumab and hyaluronidase-fihj) injection is a sterile, preservative-free, colorless to yellow, and clear to opalescent solution supplied in a single-dose vial for subcutaneous administration.

Each DARZALEX FASPRO 15 mL single-dose vial contains 1,800 mg of daratumumab and 30,000 units of hyaluronidase, L-histidine (4.9 mg), L-histidine hydrochloride monohydrate (18.4 mg), L-methionine (13.5 mg), polysorbate 20 (6 mg), sorbitol (735.1 mg), and Water for Injection, USP.

12 CLINICAL PHARMACOLOGY

12.1 Mechanism of Action

CD38 is a transmembrane glycoprotein (48 kDa) expressed on the surface of hematopoietic cells, including clonal plasma cells in multiple myeloma and light chain (AL) amyloidosis, as well as other cell types. Surface CD38 has multiple functions, including receptor mediated adhesion, signaling, and modulation of cyclase and hydrolase activity. Daratumumab is an IgG1κ human monoclonal antibody (mAb) that binds to CD38 and inhibits the growth of CD38 expressing tumor cells by inducing apoptosis directly through Fc mediated cross linking as well as by immune-mediated tumor cell lysis through complement dependent cytotoxicity (CDC), antibody dependent cell mediated cytotoxicity (ADCC) and antibody dependent cellular phagocytosis (ADCP). A subset of myeloid derived suppressor cells (CD38+MDSCs), regulatory T cells (CD38+Tregs) and B cells (CD38+Bregs) are decreased by daratumumab.

Hyaluronan is a polysaccharide found in the extracellular matrix of the subcutaneous tissue. It is depolymerized by the naturally occurring enzyme hyaluronidase. Unlike the stable structural components of the interstitial matrix, hyaluronan has a half-life of approximately 0.5 days. Hyaluronidase increases permeability of the subcutaneous tissue by depolymerizing hyaluronan. In the doses administered, hyaluronidase in DARZALEX FASPRO acts locally. The effects of hyaluronidase are reversible and permeability of the subcutaneous tissue is restored within 24 to 48 hours.

12.2 Pharmacodynamics

NK cells express CD38 and are susceptible to daratumumab mediated cell lysis. Decreases in absolute counts and percentages of total NK cells (CD16+CD56+) and activated (CD16+CD56dim) NK cells in peripheral whole blood and bone marrow were observed with DARZALEX FASPRO treatment.

Cardiac Electrophysiology

DARZALEX FASPRO as a large protein has a low likelihood of direct ion channel interactions. There is no evidence from non-clinical or clinical data to suggest that DARZALEX FASPRO has the potential to delay ventricular repolarization.

Exposure-Response Relationship

The exposure-response relationship and time course of pharmacodynamics of DARZALEX FASPRO have not been fully characterized.

12.3 Pharmacokinetics

Following the recommended dose of DARZALEX FASPRO 1,800 mg/30,000 units subcutaneously once weekly for 8 weeks, daratumumab peak concentration (Cmax) increased 4.8-fold and area under the curve (AUC0–7 days) increased 5.4-fold from the 1st dose to the 8th dose as monotherapy. Maximum trough concentrations for DARZALEX FASPRO are typically observed at the end of the weekly dosing regimens for both monotherapy and combination therapies. The mean ± standard deviation (SD) maximum trough serum concentration (Ctrough) after the 8th dose was 593 ± 306 µg/mL when DARZALEX FASPRO was administered as monotherapy in patients with multiple myeloma, 654 ± 243 µg/mL when DARZALEX FASPRO was administered as monotherapy in patients with smoldering multiple myeloma, and 537 ± 277 µg/mL, 526 ± 226 µg/mL, 756 ± 276 µg/mL, and 526 ± 209 µg/mL when DARZALEX FASPRO was administered as combination with Pd, Rd, Kd, and VRd in the PERSEUS trial, respectively. The observed mean ± SD maximum Ctrough after the 6th dose was 407 ± 183 µg/mL when DARZALEX FASPRO was administered as combination with VRd in the CEPHEUS trial.

Table 27 lists the observed mean (±SD) maximum trough concentrations (Ctrough) after the 8th dose, simulated median (5th–95th percentiles) maximum Ctrough after the 8th dose, simulated median (5th–95th percentiles) Cmax after the 8th dose, and simulated median (5th–95th percentiles) area under the curve (AUC0–7day) after the 8th dose following DARZALEX FASPRO 1,800 mg/30,000 units administered subcutaneously or daratumumab 16 mg/kg administered intravenously in patients with multiple myeloma, smoldering multiple myeloma or light chain (AL) amyloidosis. Daratumumab exposures were similar between patients treated with DARZALEX FASPRO 1,800 mg/30,000 units monotherapy and combination therapies.

Table 27: Daratumumab Exposure for Patients with Multiple Myeloma or Light Chain (AL) Amyloidosis Following 8 Weekly Doses
Parameter | Intravenous Daratumumab 16 mg/kg Monotherapy in Patients with Multiple Myeloma | DARZALEX FASPRO 1,800 mg/30,000 units Monotherapy in Patients with Multiple Myeloma | DARZALEX FASPRO 1,800 mg/30,000 units Monotherapy in Patients with Smoldering Multiple Myeloma | DARZALEX FASPRO 1,800 mg/30,000 units in combination with VRd in Patients with Transplant Eligible Multiple Myeloma | DARZALEX FASPRO 1,800 mg/30,000 units in combination with VCd in Patients with Light Chain (AL) Amyloidosis
Observed mean±SD max Ctrough after 8th dose (µg/mL) | 522±226 [Geometric mean ratio between 1,800 mg SC and 16 mg/kg was 108% (90% CI: 96, 122) in patients with multiple myeloma] | 593±306 | 654±243 | 526±209 | 597±232
Simulated median (5th–95th percentiles) max Ctrough after 8th dose (µg/mL) | 472 (144–809) | 563 (177–1063) | 690 (269–1034) | 651 (413–915) | 662 (315–1037)
Simulated median (5th–95th percentiles) Cmax after 8th dose (µg/mL) | 688 (369–1061) | 592 (234–1114) | 780 (340–1152) | 678 (431–958) | 729 (390–1105)
Simulated median (5th–95th percentiles) AUC0–7days after 8th dose (µg/mL∙day) | 4019 (1740–6370) | 4017 (1515–7564) | 5043 (2242–7426) | 4637 (2941–6522) | 4855 (2562–7522)

Absorption

At the recommended dose of DARZALEX FASPRO 1,800 mg/30,000 units, the absolute bioavailability is 69%, with peak concentrations occurring around 3 days (Tmax) in patients with multiple myeloma. Peak concentrations occurred around 4 days in patients with light chain (AL) amyloidosis.

Distribution

The estimated mean (coefficient of variation, CV) volume of distribution for the central compartment is 5.2 L (37%) and peripheral compartment was 3.8 L in patients with multiple myeloma. The estimated mean volume of distribution was 10.8 L (28%) in patients with light chain (AL) amyloidosis.

Elimination

Daratumumab is cleared by parallel linear and nonlinear saturable target mediated clearances. The estimated mean (CV%) linear clearance of daratumumab is 119 mL/day (59%) in patients with multiple myeloma and is 210 mL/day (42%) in patients with light chain (AL) amyloidosis. The estimated mean (CV%) elimination half-life associated with linear clearance is 20 days (22%) in patients with multiple myeloma and 28 days (74%) in patients with light chain (AL) amyloidosis.

Specific Populations

The following population characteristics have no clinically meaningful effect on the pharmacokinetics of daratumumab in patients administered DARZALEX FASPRO as monotherapy or as combination therapy: sex, age (33 to 92 years), renal impairment [Creatinine clearance (CLcr) 15 to 89 mL/min as determined by the Cockcroft-Gault formula], and mild hepatic impairment (total bilirubin 1 to 1.5 times ULN and AST>ULN). The effect of moderate and severe hepatic impairment on daratumumab pharmacokinetics is unknown.

Racial or Ethnic Groups

Of 190 patients with light chain (AL) amyloidosis who received DARZALEX FASPRO and had a maximum Ctrough after the 8th dose, African-Americans (4%) had 24% higher daratumumab mean maximum Ctrough after the 8th dose compared to that of Whites (83%) and Asians (10%) had 16% higher mean maximum Ctrough after the 8th dose compared to that of Whites. The difference in exposure between that of Asians and Whites could be explained in part by differences in body size. The effect of African-American race on exposure and related safety and efficacy of daratumumab is unknown.

Body Weight

In patients with multiple myeloma who received DARZALEX FASPRO 1,800 mg/30,000 units as monotherapy, the mean maximum Ctrough after the 8th dose was 12% lower in the higher body weight (BW) group (>85 kg), while the mean maximum Ctrough after the 8th dose was 81% higher in the lower BW group (≤50 kg) compared to the corresponding BW groups in the intravenous daratumumab arm.

In patients with light chain (AL) amyloidosis who received DARZALEX FASPRO 1,800 mg/30,000 units in combination and had a maximum Ctrough after the 8th dose, the mean maximum Ctrough after the 8th dose was 22% lower in the higher BW group (>85 kg), while the mean maximum Ctrough was 37% higher in the lower BW group (≤50 kg) compared to the patients with body weight of 51–85 kg.

12.6 Immunogenicity

The observed incidence of anti-drug antibody (ADA, including neutralizing antibody) is highly dependent on the sensitivity and specificity of the assay. Differences in assay methods preclude meaningful comparisons of the incidence of ADA in the studies described below with the incidence of ADA in other studies, including those of daratumumab or of other daratumumab products.

With the median DARZALEX FASPRO treatment ranging from 6.5 to 56.6 months across 9 clinical trials of patients with smoldering multiple myeloma, multiple myeloma and light chain (AL) amyloidosis treated with DARZALEX as monotherapy or as combination therapies, the incidence of anti-daratumumab antibody development was 0.6% (9/1,563) and 8 patients tested positive for neutralizing antibodies. Because of the low occurrence of anti-daratumumab antibodies, the effect of these antibodies on the pharmacokinetics, pharmacodynamics, safety, and/or effectiveness of daratumumab products is unknown.

With the median DARZALEX FASPRO treatment ranging from 6.5 to 56.5 months across 9 clinical trials of patients with smoldering multiple myeloma, multiple myeloma and light chain (AL) amyloidosis treated with DARZALEX as monotherapy or as combination therapies, the incidence of anti-rHuPH20 antibody development was 8.7% (136/1,555) and 1 patient tested positive for neutralizing antibodies. There was no identified clinically significant effect of anti-rHuPH20 antibodies on pharmacokinetics, pharmacodynamics, safety, or effectiveness of daratumumab products.

13 NONCLINICAL TOXICOLOGY

13.1 Carcinogenesis, Mutagenesis, Impairment of Fertility

No carcinogenicity or genotoxicity studies have been conducted with daratumumab. No animal studies have been performed to evaluate the potential effects of daratumumab on reproduction or development, or to determine potential effects on fertility in males or females.

No carcinogenicity, genotoxicity, or fertility studies were conducted for recombinant human hyaluronidase. There were no effects on reproductive tissues and function and no systemic exposure of hyaluronidase in monkeys given 220,000 U/kg/week subcutaneously (440 times higher than the human dose) for 39 weeks. As hyaluronidase is a recombinant form of the endogenous human hyaluronidase, no carcinogenicity, mutagenesis, or effects on fertility are expected.

14 CLINICAL STUDIES

14.1 Newly Diagnosed Multiple Myeloma

In Combination with Bortezomib, Lenalidomide and Dexamethasone in Patients Eligible for Autologous Stem Cell Transplant

The efficacy of DARZALEX FASPRO with bortezomib, lenalidomide and dexamethasone (DARZALEX FASPRO-VRd) during induction and consolidation was evaluated in PERSEUS (NCT03710603), an open-label, randomized, active-controlled trial in patients with newly diagnosed multiple myeloma eligible for ASCT. Enrollment was limited to patients 70 years of age and younger.

Patients received DARZALEX FASPRO 1,800 mg/30,000 units administered subcutaneously once weekly from weeks 1 to 8 and once every 2 weeks from weeks 9 to 16 during induction. After week 16, patients underwent stem cell mobilization, high dose chemotherapy, and ASCT. Within 12 weeks of ASCT, and when engraftment was complete, patients received DARZALEX FASPRO once every 2 weeks from weeks 1 to 8 during consolidation. Bortezomib was administered by subcutaneous injection at a dose of 1.3 mg/m^2 body surface area twice weekly for two weeks (days 1, 4, 8, and 11) of each 28-day cycle for weeks 1–16 during induction and weeks 1–8 during consolidation. Lenalidomide was administered orally at 25 mg daily (days 1–21) during weeks 1–16 during induction and weeks 1–8 during consolidation. Dexamethasone (oral or intravenous) was administered at 40 mg on Days 1–4 and Days 9–12 during weeks 1–16 during induction and weeks 1–8 during consolidation. On the days of DARZALEX FASPRO injection, the dexamethasone dose was administered orally or intravenously as a pre-injection medication. Following consolidation, patients received an investigational treatment regimen for maintenance that included DARZALEX FASPRO in combination with lenalidomide or lenalidomide alone. The trial was not designed to isolate the effect of DARZALEX FASPRO in the maintenance phase of treatment. The efficacy of DARZALEX FASPRO in combination with lenalidomide for maintenance has not been established.

The major efficacy outcome measure was progression-free survival (PFS) by independent review committee (IRC) based on IMWG response criteria.

A total of 709 patients were randomized: 355 to the DARZALEX FASPRO-VRd arm and 354 to the VRd arm. The median age was 60 years (range: 31 to 70); 59% were male, 92% were White, 1% were Black or African American, and 1% were Asian. Fifty-one percent had ISS Stage I, 34% had ISS Stage II, 15% had ISS Stage III disease. High-risk cytogenetics (presence of del(17p), t(4;14), t(14,16)) were present in 22% of patients.

PERSEUS demonstrated an improvement in PFS in the DARZALEX FASPRO-VRd arm as compared to the VRd arm; the median PFS had not been reached in either arm. Treatment with DARZALEX FASPRO-VRd resulted in a reduction in the risk of disease progression or death by 60% compared to VRd alone (HR [95% CI]: 0.40 [0.29, 0.57]; p-value < 0.0001).

Figure 1: Kaplan-Meier Curve of PFS in PERSEUS

Additional efficacy results from PERSEUS are presented in Table 28.

Table 28: Efficacy Results through End of Consolidation from PERSEUS
 | DARZALEX FASPRO-VRd (n=355) | VRd (n=354)
Overall response (sCR+CR+VGPR+PR), n (%) [Based on intent-to-treat population] | 338 (95.2%) | 326 (92.1%)
Stringent complete response (sCR) | 67 (18.9%) | 46 (13.0%)
Complete response (CR) | 91 (25.6%) | 77 (21.8%)
Very good partial response (VGPR) | 165 (46.5%) | 168 (47.5%)
Partial response (PR) | 15 (4.2%) | 35 (9.9%)
CR or better (sCR+CR), n (%) | 158 (44.5%) | 123 (34.7%)
95% CI (%) [Exact 95% confidence interval] | (39.3%, 49.9%) | (29.8%, 40.0%)
MRD negativity rate, [Based on threshold of 10^-5 using a next-generation sequencing assay (clonoSEQ)] , [Patients achieved both MRD negativity (threshold of 10^-5) and response of CR or better] , n (%) | 204 (57.5%) | 115 (32.5%)
95% CI (%) | (52.1%, 62.7%) | (27.6%, 37.6%)
MRD negativity rate in patients with CR or better, [Based on patients with CR or better response by the end of consolidation]
Number of patients with CR or better | n=158 | n=123
MRD negativity rate n (%) | 121 (76.6%) | 72 (58.5%)
95% CI (%) | (69.2%, 82.9%) | (49.3%, 67.3%)
VRd = bortezomib-lenalidomide-dexamethasone; MRD=minimal residual disease; CI=confidence interval

In Combination with Bortezomib, Lenalidomide and Dexamethasone in Patients Who Are Ineligible for ASCT

The efficacy of DARZALEX FASPRO with bortezomib, lenalidomide and dexamethasone (DARZALEX FASPRO-VRd) versus bortezomib, lenalidomide and dexamethasone (VRd) was evaluated in CEPHEUS (NCT03652064), an open-label, randomized, active-controlled trial in patients with newly diagnosed multiple myeloma who were ineligible for ASCT or refused ASCT as initial therapy.

Patients received DARZALEX FASPRO 1,800 mg/30,000 units administered subcutaneously once weekly from weeks 1 to 6, once every three weeks from weeks 7 to 24, and once every 4 weeks starting with week 25 until disease progression or unacceptable toxicity. Bortezomib was administered by subcutaneous injection at a dose of 1.3 mg/m^2 body surface area twice weekly (days 1, 4, 8, and 11) in repeated 21-day (3-week) cycles from Cycles 1–8. Lenalidomide was administered orally at 25 mg daily on Days 1–14 of Cycles 1–8 and on Days 1–21 during Cycles 9 and beyond. Dexamethasone was administered orally at 20 mg on Days 1, 2, 4, 5, 8, 9, 11, and 12 of Cycles 1–8 (or at 20 mg on Days 1, 4, 8, and 11 for patients >75 years or BMI <18.5) and at 40 mg on Days 1, 8, 15, and 22 during Cycles 9 and beyond (or at a reduced dose of 20 mg per week for patients >75 years or BMI <18.5). On the days of DARZALEX FASPRO injection, the dexamethasone dose was administered orally or intravenously as a pre-injection medication.

The effectiveness of DARZALEX FASPRO-VRd has not been established in patients who refused ASCT as initial therapy.

The major efficacy outcome measures were overall minimal residual disease (MRD) negativity rate and progression-free survival (PFS) by independent review committee (IRC) based on IMWG response criteria.

A total of 395 patients were randomized: 197 to the DARZALEX FASPRO-VRd arm and 198 to the VRd arm. The median age was 70 years (range: 31 to 80); 50% were male and 81% were White, 5% were Black or African American, and 6% were Asian. Thirty-four percent had ISS Stage I, 38% had ISS Stage II, and 28% had ISS Stage III disease. High-risk cytogenetics (presence of del(17p), t(4;14), t(14,16)) were present in 13% of patients.

The trial demonstrated a statistically significant improvement in overall MRD negativity rate, PFS, CR or better rate, and sustained MRD negativity rate, as shown in Table 29 and Figure 2.

Table 29: Efficacy Outcomes from CEPHEUS [Based on intent-to-treat population unless otherwise noted.] , [The hierarchical testing order in the CEPHEUS study was overall MRD negativity rate followed by CR or better rate, PFS, and sustained MRD negativity rate.]
 | DARZALEX FASPRO-VRd (N=197) | VRd (N=198)
PFS based on IRC [Interim analysis: Median follow-up of 39 months (cut-off date 08 September 2022).]
Number of events, n (%) | 46 (23.4%) | 68 (34.3%)
Median, months with 95% CI | NR (NE, NE) | NR (NE, NE)
Hazard ratio with 95% CI [Hazard ratio and 95% CI from a Cox proportional hazards model with treatment as the sole explanatory variable and stratified with ISS staging (I, II, III), and age/transplant eligibility (<70 years ineligible, or <70 years and refusal to transplant, or ≥70 years) as randomized. A hazard ratio <1 indicates an advantage for D-VRd.] | 0.60 (0.41, 0.88)
p-value [p-value is based on the log-rank test stratified with ISS staging (I, II, III), and age/transplant eligibility (<70 years ineligible, or <70 years and refusal to transplant, or ≥70 years) as randomized.] | 0.0078
MRD negativity rate n (%) [Primary analysis: Median follow-up of 22 months (cut-off date 08 April 2021).] , [Patients achieved both MRD negativity (threshold of 10^-5) and CR or better. All MRD testing was performed with a next-generation sequencing assay (clonoSEQ).] | 103 (52.3%) | 69 (34.8%)
p-value [p-value from Cochran Mantel-Haenszel Chi-Squared test.] | 0.0005
Overall CR or better (sCR+CR) n (%) | 150 (76.1%) | 116 (58.6%)
p-value | 0.0002
MRD negativity rate in patients with CR or better, [Patients achieving MRD negativity (threshold of 10^-5) among only patients achieving a response of CR or better.]
Number of patients with CR or better | n=150 | n=116
MRD negativity rate n (%) | 103 (68.7%) | 69 (59.5%)
95% CI (%) [Exact 95% confidence interval.] | (60.6%, 76.0%) | (50.0%, 68.5%)
Sustained MRD negativity rate n (%), [Sustained MRD negativity is defined as confirmed MRD negative status at two examinations at least 1 year apart without MRD positive status in between.] | 84 (42.6%) | 50 (25.3%)
p-value [p-value from Fisher's exact test.] | 0.0003
Overall response (sCR+CR+VGPR+PR) n(%) [Final analysis: Median follow-up of 59 months (cut-off date 07 May 2024).] | 191 (97.0%) | 185 (93.4%)
Stringent Complete Response (sCR) | 128 (65.0%) | 89 (44.9%)
Complete response (CR) | 32 (16.2%) | 33 (16.7%)
Very good partial response (VGPR) | 23 (11.7%) | 49 (24.7%)
Partial response (PR) | 8 (4.1%) | 14 (7.1%)
VRd=bortezomib-lenalidomide-dexamethasone; PFS=progression-free survival; MRD=minimal residual disease; CI=confidence interval; NR = not reached; NE = not evaluable.

Figure 2: Kaplan-Meier Curve of PFS in CEPHEUS [PFS median follow-up of 39 months]

In Combination with Bortezomib, Melphalan and Prednisone in Patients Ineligible for Autologous Stem Cell Transplant

The efficacy of DARZALEX FASPRO with bortezomib, melphalan and prednisone was evaluated in a single-arm cohort of PLEIADES (NCT03412565), a multi-cohort, open-label trial. Eligible patients were required to have newly diagnosed multiple myeloma who are ineligible for transplant. Patients received DARZALEX FASPRO 1,800 mg/30,000 units administered subcutaneously once weekly from weeks 1 to 6, once every 3 weeks from weeks 7 to 54 and once every 4 weeks starting with week 55 until disease progression or unacceptable toxicity; bortezomib 1.3 mg/m^2 subcutaneously twice weekly on Weeks 1, 2, 4 and 5 for the first 6-week cycle (Cycle 1; 8 doses), followed by once weekly on Weeks 1, 2, 4 and 5 for eight more 6-week cycles (Cycles 2–9; 4 doses per cycle); and melphalan 9 mg/m^2 and prednisone 60 mg/m^2 orally on Days 1 to 4 of the nine 6-week cycles (Cycles 1–9). The major efficacy outcome measure was overall response rate (ORR).

A total of 67 patients received DARZALEX FASPRO with VMP. The median age was 75 years (range: 66 to 86 years); 46% were male; 69% were White, 8% Asian, and 2% Black or African American; and 33% had ISS Stage I, 45% had ISS Stage II, and 22% had ISS Stage III disease.

Efficacy results are summarized in Table 30. The median duration of follow-up for patients was 6.9 months.

Table 30: Efficacy Results from PLEIADES in Patients Who Received DARZALEX FASPRO-VMP
 | DARZALEX FASPRO-VMP (N=67)
Overall response rate (sCR+CR+VGPR+PR), n (%) [Based on treated patients] | 59 (88%)
95% CI (%) | (78%, 95%)
Stringent complete response (sCR) | 5 (8%)
Complete response (CR) | 7 (10%)
Very good partial response (VGPR) | 31 (46%)
Partial response (PR) | 16 (24%)
CI=confidence interval

14.2 Relapsed/Refractory Multiple Myeloma

In Combination with Lenalidomide and Dexamethasone

The efficacy of DARZALEX FASPRO with lenalidomide and dexamethasone (DARZALEX FASPRO-Rd) was evaluated in a single-arm cohort of PLEIADES (NCT03412565), a multi-cohort, open-label trial. Patients received DARZALEX FASPRO 1,800 mg/30,000 units administered subcutaneously once weekly from weeks 1 to 8, once every 2 weeks from weeks 9 to 24 and once every 4 weeks starting with week 25 until disease progression or unacceptable toxicity with lenalidomide 25 mg once daily orally on Days 1–21 of each 28-day cycle; and dexamethasone 40 mg per week (or a reduced dose of 20 mg per week for patients >75 years or BMI <18.5). The major efficacy outcome measure was ORR.

A total of 65 patients received DARZALEX FASPRO with Rd. The median age was 69 years (range: 33 to 82 years); 69% were male; 69% were White, and 3% Black or African American; and 42% had ISS Stage I, 30% had ISS Stage II, and 28% had ISS Stage III disease. Patients had received a median of 1 prior line of therapy. A total of 52% of patients had a prior ASCT; 95% of patients received a prior PI; 59% received a prior immunomodulatory agent, including 22% who received prior lenalidomide; and 54% of patients received both a prior PI and immunomodulatory agent.

Efficacy results are summarized in Table 31. The median duration of follow-up for patients was 7.1 months.

Table 31: Efficacy Results from PLEIADES in Patients Who Received DARZALEX FASPRO-Rd
 | DARZALEX FASPRO-Rd (N=65)
Overall response rate (sCR+CR+VGPR+PR), n (%) [Based on treated patients] | 59 (91%)
95% CI (%) | (81%, 97%)
Stringent complete response (sCR) | 4 (6%)
Complete response (CR) | 8 (12%)
Very good partial response (VGPR) | 30 (46%)
Partial response (PR) | 17 (26%)
CI=confidence interval

In Combination with Pomalidomide and Dexamethasone

The efficacy of DARZALEX FASPRO with pomalidomide and dexamethasone (DARZALEX FASPRO-Pd) versus pomalidomide and dexamethasone (Pd) alone was evaluated in APOLLO (NCT03180736), an open-label, randomized, active-controlled trial. Patients received DARZALEX FASPRO 1,800 mg/30,000 units administered subcutaneously once weekly from weeks 1 to 8, once every 2 weeks from weeks 9 to 24 and once every 4 weeks starting with week 25 until disease progression or unacceptable toxicity with pomalidomide 4 mg once daily orally on Days 1–21 of each 28-day cycle; and dexamethasone 40 mg per week (or a reduced dose of 20 mg per week for patients >75 years). The major efficacy outcome measure was progression-free survival (PFS).

A total of 304 patients were randomized: 151 to the DARZALEX FASPRO-Pd arm and 153 to the Pd arm. The median age was 67 years (range: 35 to 90); 53% were male and 89% were White, <1% were Black or African American, and <1% were Asian, and 45% had ISS Stage I, 33% had ISS Stage II, and 22% had ISS Stage III disease. Patients had received a median of 2 prior lines of therapy (range 1–5), with 11% of patients having received 1 prior line of therapy and 75% of patients having received 2–3 prior lines of therapy. All patients received a prior treatment with a PI and lenalidomide, and 56% of patients received prior ASCT. The majority of patients were refractory to lenalidomide (80%), a PI (48%), or both an immunomodulatory agent and a PI (42%).

APOLLO demonstrated an improvement in PFS in the DARZALEX FASPRO-Pd treatment group as compared to the Pd treatment group; the median PFS was 12.4 months in the DARZALEX FASPRO-Pd treatment group and 6.9 months in the Pd treatment group (HR [95% CI]: 0.63 [0.47, 0.85]; p-value = 0.0018), representing a 37% reduction in the risk of disease progression or death for patients treated with DARZALEX FASPRO-Pd versus Pd.

Figure 3: Kaplan-Meier Curve of PFS in APOLLO

Additional efficacy results from APOLLO are presented in Table 32.

Table 32: Efficacy Results from APOLLO [Based on intent-to-treat population]
 | DARZALEX FASPRO-Pd (n=151) | Pd (n=153)
Overall response (sCR+CR+VGPR+PR) n (%) | 104 (68.9%) | 71 (46.4%)
P-value [p-value from Cochran Mantel-Haenszel Chi-Squared test adjusted for stratification factors] | <0.0001
Stringent complete response (sCR) | 14 (9.3%) | 2 (1.3%)
Complete response (CR) | 23 (15.2%) | 4 (2.6%)
Very good partial response (VGPR) | 40 (26.5%) | 24 (15.7%)
Partial response (PR) | 27 (17.9%) | 41 (26.8%)
MRD negativity rate [Based on the intent-to-treat population] , [Based on threshold of 10^-5 using a next-generation sequencing assay (clonoSEQ).] n (%) | 13 (8.6%) | 3 (2.0%)
95% CI (%) | (4.7%, 14.3%) | (0.4%, 5.6%)
P-value [p-value from Fisher's exact test.] | 0.0102
MRD negativity rate in patients with CR or better
Number of patients with CR or better | N=37 | N=6
MRD negativity rate n (%) | 13 (35.1%) | 3 (50.0%)
95% CI (%) | (20.2%, 52.5%) | (11.8%, 88.2%)
Pd=pomalidomide-dexamethasone; MRD=minimal residual disease; CI=confidence interval

In responders, the median time to response was 1 month (range: 0.9 to 9.1 months) in the DARZALEX FASPRO-Pd group and 1.9 months (range: 0.9 to 17.3 months) in the Pd group. The median duration of response had not been reached in the DARZALEX FASPRO-Pd group (range: 1 to 34.9+ months) and was 15.9 months (range: 1+ to 24.8 months) in the Pd group.

With a median follow-up of 16.9 months, 99 deaths were observed; 48 in the DARZALEX FASPRO-Pd group and 51 in the Pd group. Median OS was not reached for either treatment group.

In Combination with Carfilzomib and Dexamethasone

The efficacy of DARZALEX FASPRO with carfilzomib and dexamethasone (DARZALEX FASPRO-Kd) was evaluated in a single-arm cohort of PLEIADES (NCT03412565), a multi-cohort, open-label trial. This cohort enrolled patients with relapsed or refractory multiple myeloma excluding patients with left ventricular ejection fraction (LVEF) less than 40%, myocardial infarction within 6 months, uncontrolled cardiac arrhythmia, or uncontrolled hypertension (systolic blood pressure >159 mmHg or diastolic >99 mmHg despite optimal treatment). Patients received DARZALEX FASPRO 1,800 mg/30,000 units administered subcutaneously once weekly from Weeks 1 to 8, once every 2 weeks from Weeks 9 to 24 and once every 4 weeks starting with Week 25 until disease progression or unacceptable toxicity with carfilzomib administered by IV infusion at a dose of 20 mg/m^2 on Cycle 1 Day 1 and if a dose of 20 mg/m^2 was tolerated, carfilzomib was administered at a dose of 70 mg/m^2 as a 30-minute IV infusion, on Cycle 1 Day 8 and Day 15, and then Day 1, 8 and 15 of each cycle and dexamethasone 40 mg per week (or a reduced dose of 20 mg per week for patients ≥75 years or BMI <18.5). The major efficacy outcome measure was ORR.

A total of 66 patients received DARZALEX FASPRO with Kd. The median age was 61 years (range: 42 to 84); 52% were male; 73% were White and 3% Black or African American; and 68% had ISS Stage I, 18% had ISS Stage II, and 14% had ISS Stage III disease. A total of 79% of patients had a prior ASCT; 91% of patients received a prior PI. All patients received 1 prior line of therapy with exposure to lenalidomide and 62% of patients were refractory to lenalidomide.

Efficacy results are summarized in Table 33. At a median follow-up of 9.2 months, the median duration of response had not been reached and an estimated 85.2% (95% CI: 72.5, 92.3) maintained response for at least 6 months and 82.5% (95% CI: 68.9, 90.6) maintained response for at least 9 months.

Table 33: Efficacy Results from PLEIADES in Patients Who Received DARZALEX FASPRO-Kd
 | DARZALEX FASPRO-Kd (N=66)
Overall response rate (sCR+CR+VGPR+PR), n (%) [Based on treated patients] | 56 (84.8%)
95% CI (%) | (73.9%, 92.5%)
Stringent complete response (sCR) | 11 (16.7%)
Complete response (CR) | 14 (21.2%)
Very good partial response (VGPR) | 26 (39.4%)
Partial response (PR) | 5 (7.6%)
CI=confidence interval

Monotherapy

The efficacy of DARZALEX FASPRO as monotherapy was evaluated in COLUMBA (NCT03277105), an open-label, randomized, non-inferiority study. Eligible patients were required to have relapsed or refractory multiple myeloma who had received at least 3 prior lines of therapy including a proteasome inhibitor and an immunomodulatory agent or who were double-refractory to a proteasome inhibitor and an immunomodulatory agent. Patients were randomized to receive DARZALEX FASPRO 1,800 mg/30,000 units administered subcutaneously or daratumumab 16 mg/kg administered intravenously; each administered once weekly from weeks 1 to 8, once every 2 weeks from weeks 9 to 24 and once every 4 weeks starting with week 25 until unacceptable toxicity or disease progression. The major efficacy outcome measures were ORR by the IMWG response criteria and maximum Ctrough at pre-dose Cycle 3 Day 1 [see Clinical Pharmacology (12.3)]. Randomization was stratified by body weight, myeloma type, and number of prior lines of therapy.

A total of 522 patients were randomized: 263 to the DARZALEX FASPRO arm and 259 to the intravenous daratumumab arm. The median age was 67 years (range: 33 to 92 years); 55% were male; and 78% were White, 14% Asian, and 3% Black or African American. The median weight was 73 kg (range: 29 to 138). Patients had received a median of 4 prior lines of therapy. A total of 51% of patients had a prior ASCT; 100% of patients received both a PI and an immunomodulatory agent. Forty-nine percent of patients were refractory both a PI and an immunomodulatory agent. Eighty-two percent of patients were refractory to their last line of prior systemic therapy.

The results show that DARZALEX FASPRO 1,800 mg/30,000 units administered subcutaneously is non-inferior to daratumumab 16 mg/kg administered intravenously in terms of ORR and maximum trough concentration [see Clinical Pharmacology (12.3)]. Median progression-free survival was 5.6 months in the DARZALEX FASPRO arm and 6.1 months in the intravenous daratumumab arm. ORR results are provided in Table 34.

Table 34: Efficacy Results from COLUMBA
 | DARZALEX FASPRO (N=263) | Intravenous Daratumumab (N=259)
Overall response (sCR+CR+VGPR+PR), n (%) [Based on intent-to-treat population.] | 108 (41%) | 96 (37%)
95% CI (%) | (35%, 47%) | (31%, 43%)
Ratio of response rates (95% CI) |  | 1.11 (0.89, 1.37)
CR or better, n (%) | 5 (1.9%) | 7 (2.7%)
Very good partial response (VGPR) | 45 (17%) | 37 (14%)
Partial response (PR) | 58 (22%) | 52 (20%)

14.3 High-Risk Smoldering Multiple Myeloma

Monotherapy

The efficacy of DARZALEX FASPRO as monotherapy versus active monitoring was evaluated in AQUILA (NCT03301220), an open-label, randomized trial in patients with high-risk smoldering multiple myeloma.

Patients randomized to the treatment arm received DARZALEX FASPRO 1,800 mg/30,000 units administered subcutaneously once weekly from weeks 1 to 8, once every 2 weeks from weeks 9 to 24 and once every 4 weeks starting with week 25 until 39 cycles or up to 36 months or until diagnosis to multiple myeloma or unacceptable toxicity.

The major efficacy outcome measure was progression-free survival (PFS) by independent review committee (IRC) as defined as the diagnosis of multiple myeloma based on the IMWG diagnostic criteria for multiple myeloma or death.

A total of 390 patients were randomized: 194 to the DARZALEX FASPRO arm and 196 to the active monitoring arm. The median age was 64 years (range: 31 to 86); 12% were ≥75 years; 48% were male; 83% White, 8% Asian, and 3% were Black or African American. Forty-one percent of patients had 2 or more of the following criteria for high-risk smoldering multiple myeloma: serum monoclonal protein level >2 g/dL, involved-to-uninvolved serum-free light chain ratio >20, and bone marrow plasma cells >20%. DARZALEX FASPRO is only indicated for patients with high-risk smoldering multiple myeloma. It is not indicated for other risk categories.

PFS results are shown in Figure 4.

Figure 4: Kaplan-Meier Curve of PFS in AQUILA

Additional efficacy results from AQUILA are presented in Table 35.

Table 35: Efficacy Results from AQUILA [Based on intent-to-treat population per investigator assessment]
 | DARZALEX FASPRO (n=194) | Active Monitoring (n=196)
Overall response (sCR+CR+VGPR+PR), n (%) | 123 (63.4%) | 2 (1.0%)
Stringent complete response (sCR) | 7 (3.6%) | 0
Complete response (CR) | 10 (5.2%) | 0
Very good partial response (VGPR) | 41 (21.1%) | 1 (0.5%)
Partial response (PR) | 65 (33.5%) | 1 (0.5%)

14.4 Light Chain Amyloidosis

In Combination with Bortezomib, Cyclophosphamide and Dexamethasone

The efficacy of DARZALEX FASPRO with VCd was evaluated in ANDROMEDA (NCT03201965), an open-label, randomized, active-controlled trial. Eligible patients were required to have newly diagnosed light chain (AL) amyloidosis with at least one affected organ, measurable hematologic disease, Cardiac Stage I–IIIA (based on European Modification of Mayo 2004 Cardiac Stage), and NYHA Class I–IIIA. Patients with NYHA Class IIIB and IV were excluded. Patients were randomized to receive bortezomib 1.3 mg/m^2 administered subcutaneously, cyclophosphamide 300 mg/m^2 (max dose 500 mg) administered orally or intravenously, and dexamethasone 40 mg (or a reduced dose of 20 mg for patients >70 years or body mass index <18.5 or who have hypervolemia, poorly controlled diabetes mellitus or prior intolerance to steroid therapy) administered orally or intravenously on Days 1, 8, 15, and 22 of each 28-day cycle with or without DARZALEX FASPRO 1,800 mg/30,000 units subcutaneously once weekly from weeks 1 to 8, once every 2 weeks from weeks 9 to 24 and once every 4 weeks starting with week 25 until disease progression or a maximum of two years. When DARZALEX FASPRO and dexamethasone were administered on the same day, dexamethasone 20 mg was administered before DARZALEX FASPRO with the remaining dose of dexamethasone administered after DARZALEX FASPRO if applicable. The major efficacy outcome measure was confirmed hematologic complete response (HemCR) rate based on Consensus Criteria as determined by the Independent Review Committee (negative serum and urine immunofixation, involved free light chain level decrease to less than the upper limit of normal, and normal free light chain ratio). Randomization was stratified by Cardiac Stage (European Modification of Mayo 2004 Cardiac Stage) countries that typically offer autologous stem cell transplant (ASCT) for patients with light chain (AL) amyloidosis, and renal function.

A total of 388 patients were randomized: 195 to DARZALEX FASPRO-VCd and 193 to VCd. The median patient age was 64 years (range: 34 to 87 years); 58% were male; 76% White, 17% Asian, and 3% Black or African American; 23% had light chain (AL) amyloidosis Cardiac Stage I, 40% had Stage II, and 37% had Stage IIIA. The median number of organs involved was 2 (range: 1–6) and 66% of patients had 2 or more organs involved. Vital organ involvement was: cardiac 71%, renal 59% and hepatic 8%. The majority (79%) of patients had lambda free light chain disease.

Efficacy results are summarized in Table 36.

Table 36: Efficacy Results from ANDROMEDA [All results from the planned analysis after a median follow-up of 11.4 months based on intent-to-treat population]
 | DARZALEX FASPRO-VCd (n=195) | VCd (n=193)
Hematologic complete response (HemCR), n (%) | 82 (42%) | 26 (13%)
p-value [p-value from Cochran Mantel-Haenszel Chi-Squared test.] | <0.0001
Very good partial response (VGPR), n (%) | 71 (36%) | 69 (36%)
Partial response (PR), n (%) | 26 (13%) | 53 (27%)
Hematologic VGPR or better (HemCR + VGPR), n (%) | 153 (78%) | 95 (49%)
Major organ deterioration progression-free survival [Major organ deterioration-PFS defined as hematologic progression, major organ (cardiac or renal) deterioration or death] , Hazard ratio with 95% CI | 0.58 (0.37, 0.92)
VCd=bortezomib-cyclophosphamide-dexamethasone

The median time to HemCR was 59 days (range: 8 to 299 days) in the DARZALEX FASPRO-VCd arm and 59 days (range: 16 to 340 days) in the VCd arm. The median time to VGPR or better was 17 days (range: 5 to 336 days) in the DARZALEX FASPRO-VCd arm and 25 days (range: 8 to 171 days) in the VCd arm. The median duration of HemCR had not been reached in either arm.

After a median follow-up of 61.4 months, ANDROMEDA demonstrated an improvement in major organ deterioration progression free survival (MOD-PFS) in the DARZALEX FASPRO-VCd arm as compared to the VCd arm (HR=0.47; 95% CI: 0.33, 0.67; p<0.0001), representing a 53% reduction in the risk of hematologic progression, major organ deterioration, or death in patients treated in the DARZALEX FASPRO-VCd arm. The median MOD-PFS was not reached in the DARZALEX FASPRO-VCd arm and was 30.2 months in the VCd arm.

Figure 5: Kaplan-Meier Curve of MOD-PFS in ANDROMEDA

After a median follow-up of 61.4 months, ANDROMEDA demonstrated an improvement in overall survival (OS) in the DARZALEX FASPRO-VCd arm as compared to the VCd arm (HR=0.62; 95% CI: 0.42, 0.90; p=0.0121), representing a 38% reduction in the risk of death in patients treated in the DARZALEX FASPRO-VCd arm. The median OS had not been reached in either arm.

Figure 6: Kaplan-Meier Curve of OS in ANDROMEDA

15 REFERENCES

1. Chapuy, CI, RT Nicholson, MD Aguad, et al., 2015, Resolving the daratumumab interference with blood compatibility testing, Transfusion, 55:1545–1554 (accessible at http://onlinelibrary.wiley.com/doi/10.1111/trf.13069/epdf).

16 HOW SUPPLIED/STORAGE AND HANDLING

DARZALEX FASPRO® (daratumumab and hyaluronidase-fihj) injection is a sterile, preservative-free, colorless to yellow, and clear to opalescent solution for subcutaneous use supplied as individually packaged single-dose vials providing 1,800 mg of daratumumab and 30,000 units of hyaluronidase per 15 mL (NDC 57894-503-01).

STORAGE AND HANDLING

Store DARZALEX FASPRO vials in a refrigerator at 2ºC to 8ºC (36ºF to 46ºF) in the original carton to protect from light.

Do not freeze or shake.

17 PATIENT COUNSELING INFORMATION

Advise the patient to read the FDA-approved patient labeling (Patient Information).

Hypersensitivity and Other Administration Reactions

Advise patients to seek immediate medical attention for any of the following signs and symptoms of systemic administration-related reactions: itchy, runny or blocked nose; chills, nausea, throat irritation, cough, headache, shortness of breath or difficulty breathing, and blurred vision [see Warnings and Precautions (5.1)].

Cardiac Toxicity in Patients with Light Chain (AL) Amyloidosis

Advise patients to immediately contact their healthcare provider if they have signs or symptoms of cardiac adverse reactions [see Warnings and Precautions (5.2)].

Infections

Inform patients about the risk of developing infections during DARZALEX FASPRO treatment, and to report immediately any fever or symptoms of infection to their healthcare provider [see Warnings and Precautions (5.3)].

Neutropenia

Advise patients to contact their healthcare provider if they have a fever [see Warnings and Precautions (5.4)].

Thrombocytopenia

Advise patients to contact their healthcare provider if they have bruising or bleeding [see Warnings and Precautions (5.5)].

Embryo-Fetal Toxicity

Advise pregnant women of the potential hazard to a fetus. Advise females of reproductive potential to inform their healthcare provider of a known or suspected pregnancy [see Warnings and Precautions (5.6), Use in Specific Populations (8.1, 8.3)].

Advise females of reproductive potential to use effective contraception during treatment with DARZALEX FASPRO and for 3 months after the last dose [see Use in Specific Populations (8.1, 8.3)].

Advise patients that lenalidomide, thalidomide and pomalidomide have the potential to cause fetal harm and have specific requirements regarding contraception, pregnancy testing, blood and sperm donation, and transmission in sperm. Lenalidomide, thalidomide and pomalidomide are only available through a REMS program [see Use in Specific Populations (8.1, 8.3)].

Interference with Laboratory Tests

Advise patients to inform their healthcare provider, including personnel at blood transfusion centers, that they are taking DARZALEX FASPRO, in the event of a planned transfusion [see Warnings and Precautions (5.7)].

Advise patients that DARZALEX FASPRO can affect the results of some tests used to determine complete response in some patients and additional tests may be needed to evaluate response [see Warnings and Precautions (5.8)].

Hepatitis B Virus (HBV) Reactivation

Advise patients to inform healthcare providers if they have ever had or might have a hepatitis B infection and that DARZALEX FASPRO could cause hepatitis B virus to become active again [see Adverse Reactions (6.1)].

Manufactured by:
Janssen Biotech, Inc.
Horsham, PA 19044, USA
U.S. License Number 1864

For patent information: www.janssenpatents.com

© Janssen Pharmaceutical Companies, 2021

PATIENT INFORMATION
DARZALEX (Dar-zah-lex) FASPRO® (Fas-pro)
(daratumumab and hyaluronidase-fihj)
injection, for subcutaneous use

DARZALEX FASPRO may be used with other medicines called lenalidomide, thalidomide or pomalidomide. You should also read the Medication Guide that comes with lenalidomide, thalidomide or pomalidomide if you use DARZALEX FASPRO with these medicines.

What is DARZALEX FASPRO?
DARZALEX FASPRO is a prescription medicine used:

- to treat adults with multiple myeloma:
  - in combination with the medicines bortezomib, lenalidomide, and dexamethasone in newly diagnosed people who are eligible to receive a type of stem cell transplant that uses their own stem cells (autologous stem cell transplant).
  - in combination with the medicines bortezomib, lenalidomide, and dexamethasone in newly diagnosed people who cannot receive a type of stem cell transplant that uses their own stem cells (autologous stem cell transplant).
  - in combination with the medicines bortezomib, melphalan and prednisone, in newly diagnosed people who cannot receive a type of stem cell transplant that uses their own stem cells (autologous stem cell transplant).
  - in combination with the medicines lenalidomide and dexamethasone in newly diagnosed people who cannot receive a type of stem cell transplant that uses their own stem cells (autologous stem cell transplant) and in people whose multiple myeloma has come back or did not respond to treatment, who have received at least one prior medicine.
  - in combination with the medicines bortezomib, thalidomide, and dexamethasone in newly diagnosed people who are eligible to receive a type of stem cell transplant that uses their own stem cells (autologous stem cell transplant).
  - in combination with the medicines bortezomib and dexamethasone in people who have received at least one prior medicine.
  - in combination with the medicines pomalidomide and dexamethasone in people who have received at least one prior medicine including lenalidomide and a proteasome inhibitor.
  - in combination with the medicines carfilzomib and dexamethasone in people whose multiple myeloma has come back or did not respond to treatment who have received one to three prior medicines.
  - alone in people who have received at least three prior medicines, including a proteasome inhibitor and an immunomodulatory agent, or did not respond to a proteasome inhibitor and an immunomodulatory agent.
- alone to treat adults with high-risk smoldering multiple myeloma (an early form of multiple myeloma that has a higher chance of progressing to active multiple myeloma).
- in combination with the medicines bortezomib, cyclophosphamide and dexamethasone to treat adults with newly diagnosed light chain (AL) amyloidosis.

It is not known if DARZALEX FASPRO is safe and effective in children.

Do not receive DARZALEX FASPRO if you have a history of a severe allergic reaction to daratumumab, hyaluronidase or any of the ingredients in DARZALEX FASPRO. See the end of this leaflet for a complete list of ingredients in DARZALEX FASPRO.

Before you receive DARZALEX FASPRO, tell your healthcare provider about all of your medical conditions, including if you:

- have a history of breathing problems.
- have had shingles (herpes zoster).
- have ever had or might now have a hepatitis B infection as DARZALEX FASPRO could cause hepatitis B virus to become active again. Your healthcare provider will check you for signs of this infection before, during and for some time after treatment with DARZALEX FASPRO. Tell your healthcare provider right away if you get worsening tiredness or yellowing of your skin or white part of your eyes.
- are pregnant or plan to become pregnant. DARZALEX FASPRO may harm your unborn baby. Tell your healthcare provider right away if you become pregnant or think that you may be pregnant during treatment with DARZALEX FASPRO.
  - Females who are able to become pregnant should use an effective method of birth control (contraception) during treatment and for 3 months after your last dose of DARZALEX FASPRO. Talk to your healthcare provider about birth control methods that you can use during this time.
  - Before starting DARZALEX FASPRO in combination with lenalidomide, thalidomide or pomalidomide, females and males must agree to the instructions in the lenalidomide, thalidomide or pomalidomide REMS program.
    - The lenalidomide, thalidomide and pomalidomide REMS have more information about effective methods of birth control, pregnancy testing, and blood donation for females who can become pregnant.
    - For males who have female partners who can become pregnant, there is information in the lenalidomide, thalidomide and pomalidomide REMS about sperm donation and how lenalidomide, thalidomide and pomalidomide can pass into human semen.
- are breastfeeding or plan to breastfeed. It is not known if DARZALEX FASPRO passes into your breast milk. You should not breastfeed during treatment with DARZALEX FASPRO. Talk to your healthcare provider about the best way to feed your baby during treatment with DARZALEX FASPRO.

Before you receive DARZALEX FASPRO for light chain (AL) amyloidosis, tell your healthcare provider if you have a history of heart problems. DARZALEX FASPRO should not be used in light chain (AL) amyloidosis patients with highly advanced heart disease outside of clinical trials.
Tell your healthcare provider about all the medicines you take, including prescription and over-the-counter medicines, vitamins, and herbal supplements.

How will I receive DARZALEX FASPRO?

- DARZALEX FASPRO may be given alone to treat multiple myeloma or high-risk smoldering multiple myeloma or together with other medicines to treat multiple myeloma or light chain (AL) amyloidosis.
- DARZALEX FASPRO will be given to you by your healthcare provider as an injection under the skin, in the stomach area (abdomen).
- DARZALEX FASPRO is injected over 3 to 5 minutes.
- Your healthcare provider will decide the time between doses as well as how many treatments you will receive.
- Your healthcare provider will give you medicines before each dose of DARZALEX FASPRO and after each dose of DARZALEX FASPRO to help reduce the risk of serious allergic reactions and other reactions due to release of certain substances by your body (systemic).

If you miss any appointments, call your healthcare provider as soon as possible to reschedule your appointment.

What are the possible side effects of DARZALEX FASPRO?
DARZALEX FASPRO may cause serious reactions, including:

- Serious allergic reactions and other severe injection-related reactions. Serious allergic reactions and reactions due to release of certain substances by your body (systemic) that can lead to death, can happen with DARZALEX FASPRO. Your healthcare provider may temporarily stop or completely stop treatment with DARZALEX FASPRO if you have a serious reaction. Tell your healthcare provider or get medical help right away if you get any of these symptoms during or after an injection of DARZALEX FASPRO.

- shortness of breath or trouble breathing
- dizziness or lightheadedness (hypotension)
- cough
- wheezing
- heart beating faster than usual
- low oxygen in the blood (hypoxia)

- throat tightness or irritation
- runny or stuffy nose
- headache
- itching
- high blood pressure
- eye pain

- nausea
- vomiting
- chills
- fever
- chest pain
- blurred vision

- Injection site reactions. Skin reactions at or near the injection site (local), including injection site reactions, can happen with DARZALEX FASPRO. Symptoms at the site of injection may include itching, swelling, bruising, pain, rash, bleeding, or redness of the skin. These reactions sometimes happen more than 24 hours after an injection of DARZALEX FASPRO.
- Heart problems in people with light chain (AL) amyloidosis. Heart problems, in some cases fatal, have occurred. Your healthcare provider will monitor you closely during treatment with DARZALEX FASPRO. Call your healthcare provider right away if you get any of the following symptoms: chest pain, feeling faint, swollen legs, shortness of breath, or abnormal heart rhythm.
- Infections. DARZALEX FASPRO can cause serious life-threatening infections that can lead to death. Tell your healthcare provider right away if you develop a fever, trouble breathing, cough, burning or pain when you urinate, or any other signs and symptoms of infection during treatment.
- Decreases in blood cell counts. DARZALEX FASPRO can decrease white blood cell counts which help fight infections and blood cells called platelets which help to clot blood. Decreases in blood cell counts are common with DARZALEX FASPRO and can be severe. Your healthcare provider will check your blood cell counts during treatment with DARZALEX FASPRO. Tell your healthcare provider if you develop fever or have signs of bruising or bleeding.
- Changes in blood tests. DARZALEX FASPRO can affect the results of blood tests to match your blood type. These changes can last for up to 6 months after your final dose of DARZALEX FASPRO. Your healthcare provider will do blood tests to match your blood type before you start treatment with DARZALEX FASPRO. Tell all of your healthcare providers that you are being treated with DARZALEX FASPRO before receiving blood transfusions.

The most common side effects of DARZALEX FASPRO when used alone include:

- cold-like symptoms (upper respiratory tract infection)
- muscle, bone, and joint pain
- tiredness
- diarrhea
- rash

- trouble sleeping, including sleep apnea and restless legs
- nerve problems, including increased or decreased sensitivity to touch, temperature, or pain; loss of smell; and numbness, tingling, or burning sensations
- injection site reactions

The most common side effects of DARZALEX FASPRO when used in combination therapy include:

- tiredness
- nausea
- diarrhea
- shortness of breath
- trouble sleeping
- headache
- rash
- kidney problems
- movement and balance problems, muscle spasms, weakness, and tremors

- fever
- cough
- muscle spasms
- back pain
- vomiting
- high blood pressure
- muscle, bone, and joint pain
- decreased appetite
- urinary tract infection
- stomach pain
- cold-like symptoms (upper respiratory tract infection)

- nerve problems, including increased or decreased sensitivity to touch, temperature, or pain; loss of smell; and numbness, tingling, or burning sensations
- constipation
- lung infection (pneumonia)
- swollen hands, ankles, or feet
- feeling dizzy
- bruising
- COVID-19

The most common severe abnormal blood test results with DARZALEX FASPRO include decreased white blood cells, platelets, and red blood cells.

These are not all of the possible side effects of DARZALEX FASPRO.
Call your doctor for medical advice about side effects. You may report side effects to FDA at 1-800-FDA-1088.

General information about the safe and effective use of DARZALEX FASPRO.
Medicines are sometimes prescribed for purposes other than those listed in a Patient Information leaflet. You can ask your pharmacist or healthcare provider for information about DARZALEX FASPRO that is written for health professionals.

What are the ingredients in DARZALEX FASPRO?
Active ingredient: daratumumab and hyaluronidase-fihj
Inactive ingredients: L-histidine, L-histidine hydrochloride monohydrate, L-methionine, polysorbate 20, sorbitol, and water for injection.
Manufactured by: Janssen Biotech, Inc., Horsham, PA 19044, USA
U.S. License Number 1864
For patent information: www.janssenpatents.com
©Janssen Pharmaceutical Companies, 2021
For more information, call 1-800-526-7736 or go to www.DARZALEXFASPRO.com.

This Patient Information has been approved by the U.S. Food and Drug Administration.

Revised: 1/2026

PRINCIPAL DISPLAY PANEL - 15 mL Vial Box

NDC 57894-503-01

DARZALEX Faspro®
(daratumumab and
hyaluronidase-fihj)
Injection

1,800 mg and
30,000 Units/15 mL
(120 mg and 2,000 Units/mL)

For Subcutaneous Use Only

Administer subcutaneous
injection over 3 to 5 minutes.

Rx only

One 15 mL Vial

Single-dose vial.
Discard unused portion.

janssen